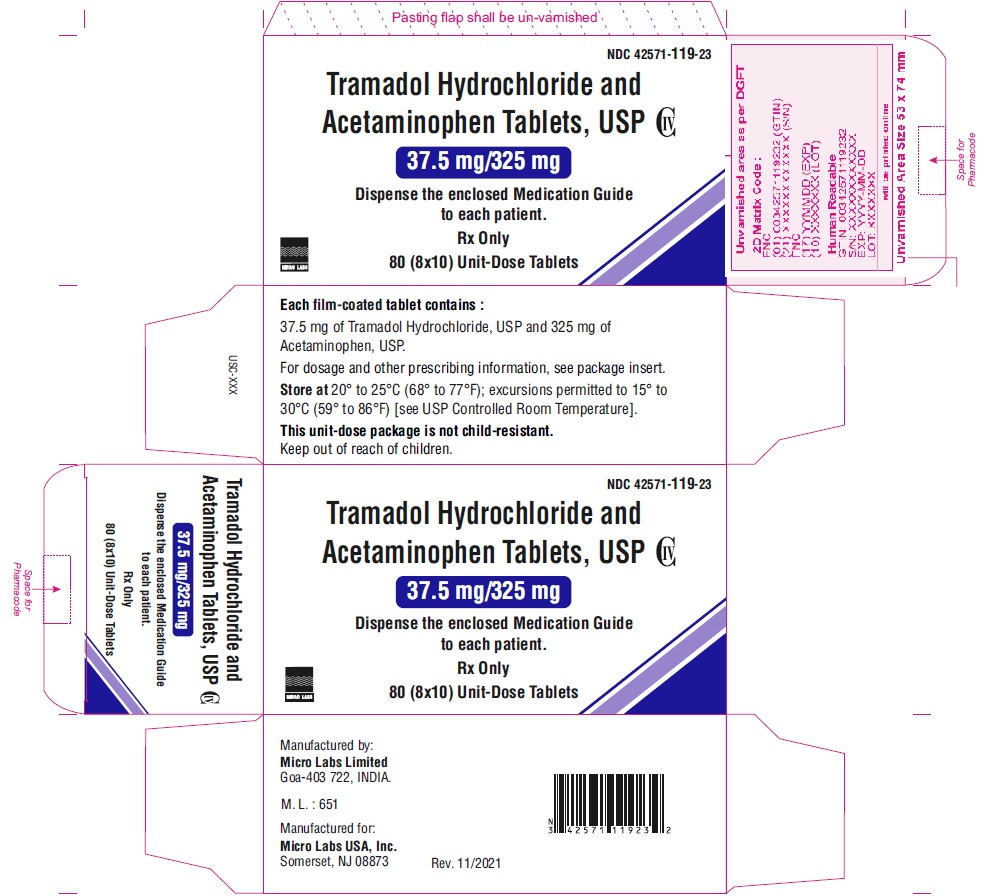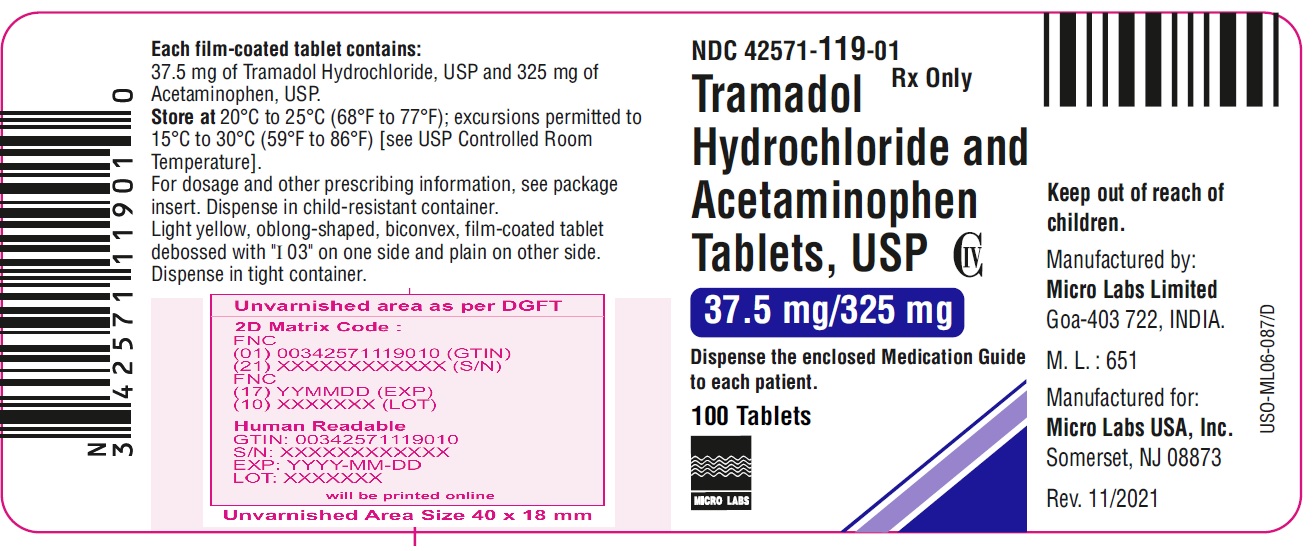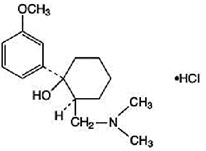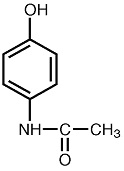 DRUG LABEL: TRAMADOL HYDROCHLORIDE AND ACETAMINOPHEN

NDC: 42571-119 | Form: TABLET, FILM COATED
Manufacturer: Micro Labs Limited
Category: prescription | Type: HUMAN PRESCRIPTION DRUG LABEL
Date: 20251222
DEA Schedule: CIV

ACTIVE INGREDIENTS: TRAMADOL HYDROCHLORIDE 37.5 mg/1 1; ACETAMINOPHEN 325 mg/1 1
INACTIVE INGREDIENTS: STARCH, CORN; POWDERED CELLULOSE; SODIUM STARCH GLYCOLATE TYPE A POTATO; MAGNESIUM STEARATE; TITANIUM DIOXIDE; POLYETHYLENE GLYCOL 400; FERRIC OXIDE YELLOW; POLYSORBATE 80; HYPROMELLOSE 2910 (3 MPA.S); HYPROMELLOSE 2910 (6 MPA.S)

HIGHLIGHTS OF PRESCRIBING INFORMATION

These highlights do not include all the information needed to use TRAMADOL HYDROCHLORIDE AND ACETAMINOPHEN TABLETS safely and effectively. See full prescribing information for TRAMADOL HYDROCHLORIDE AND ACETAMINOPHEN TABLETS.
TRAMADOL HYDROCHLORIDE and ACETAMINOPHEN tablets, for oral use, C-IV
Initial U.S. Approval: 2001

RECENT MAJOR CHANGES

Boxed Warning 08/2025

Indications and Usage (1) 08/2025

Dosage and Administration (2.2, 2.5) 10/2025

- 2.2 Patient Access to an Opioid Overdose Reversal Agent for the Emergency Treatment of Opioid Overdose
- 2.5 Safe Reduction or Discontinuation of Tramadol Hydrochloride and Acetaminophen Tablets

Warnings and Precautions (5.1, 5.2, 5.3, 5.18, 5.21) 10/2025

- 5.1 Addiction, Abuse, and Misuse
- 5.2 Life-Threatening Respiratory Depression
- 5.3 Risks from Concomitant Use with Benzodiazepines or Other CNS Depressants
- 5.18 Risk of Gastrointestinal Complications
- 5.21 Withdrawal

WARNING: SERIOUS AND LIFE-THREATENING RISKS FROM USE OF TRAMADOL HYDROCHLORIDE AND ACETAMINOPHEN TABLETS

See full prescribing information for complete boxed warning.

- Tramadol hydrochloride and acetaminophen tablet exposes users to the risks of addiction, abuse and misuse, which can lead to overdose and death. Assess each patient’s risk prior to prescribing tramadol hydrochloride and acetaminophen tablets, and monitor regularly for these behaviors or conditions. (5.1)
- Serious, life-threatening, or fatal respiratory depression may occur. Monitor closely, especially during initiation or following a dose increase. (5.2)
- Accidental ingestion of tramadol hydrochloride and acetaminophen tablets, especially by children, can result in a fatal overdose of tramadol. (5.2)
- Concomitant use of opioids with benzodiazepines or other central nervous system (CNS) depressants, including alcohol, may result in profound sedation, respiratory depression, coma, and death. Reserve concomitant prescribing for use in patients for whom alternative treatment options are inadequate; limit dosages and durations to the minimum required; and follow patients for signs and symptoms of respiratory depression and sedation. (5.3, 7)
- Advise pregnant women using opioids for an extended period of time of the risk of Neonatal Opioid Withdrawal Syndrome, which may be life-threatening if not recognized and treated. Ensure that management by neonatology experts will beavailable at delivery. (5.4)
- To ensure that the benefits of opioid analgesics outweigh the risks of addiction, abuse, and misuse, the Food and Drug Administration (FDA) has required a Risk Evaluation and Mitigation Strategy (REMS) for these products. (5.5)
- Life-threatening respiratory depression and death have occurred in children who received tramadol. Some of the reported cases followed tonsillectomy and/or adenoidectomy; in at least one case, the child had evidence of being an ultra-rapid metabolizer of tramadol due to a CYP2D6 polymorphism (5.6).
- Tramadol hydrochloride and acetaminophen tablet is contraindicated in children younger than 12 years of age and in children younger than 18 years of age following tonsillectomy and/or adenoidectomy (4). Avoid the use of tramadol hydrochloride and acetaminophen tablets in adolescents 12 to 18 years of age who have other risk factors that may increase their sensitivity to the respiratory depressant effects of tramadol. (5.6)
- The effects of concomitant use or discontinuation of cytochrome P450 3A4 inducers, 3A4 inhibitors, or 2D6 inhibitors with tramadol are complex. Use of cytochrome P450 3A4 inducers, 3A4 inhibitors, or 2D6 inhibitors with tramadol hydrochloride and acetaminophen tablets requires careful consideration of the effects on the parent drug, tramadol, and the active metabolite, M1. (5.7, 7)

- Tramadol hydrochloride and acetaminophen tablet contains acetaminophen. Acetaminophen has been associated with cases of acute liver failure, at times resulting in liver transplant and death. Most of the cases of liver injury are associated with the use of acetaminophen at doses that exceed 4,000 milligrams per day, and often involve more than one acetaminophen containing product. (5.9)

1 INDICATIONS AND USAGE

Tramadol hydrochloride and acetaminophen tablet is a combination of tramadol hydrochloride, an opioid agonist, and acetaminophen, and is indicated for the management of acute pain, severe enough to require an opioid analgesic and for which alternative treatments are inadequate. (1)

Limitations of Use

Tramadol hydrochloride and acetaminophen tablets are indicated for short-term use of five days or less.

- Because of the risks of addiction, abuse, misuse, overdose, and death, which can occur at any dosage or duration and persist over the course of therapy, reserve opioid analgesics, including tramadol hydrochloride and acetaminophen tablets for use in patients for whom alternative treatment options are ineffective, not tolerated, or would be otherwise inadequate to provide sufficient management of pain. (1, 5.1)

2 DOSAGE AND ADMINISTRATION

- Tramadol hydrochloride and acetaminophen tablets should be prescribed only by healthcare professionals who are knowledgeable about the use of opioids and how to mitigate the associated risks. (2.1)
- Use the lowest effective dosage for the shortest duration of time consistent with individual patient treatment goals. Reserve titration to higher doses of tramadol hydrochloride and acetaminophen tablets for patients in whom lower doses are insufficiently effective and in whom the expected benefits of using a higher dose opioid clearly outweigh the substantial risks. (2.1, 5)
- Many acute pain conditions (e.g., the pain that occurs with a number of surgical procedures or acute musculoskeletal injuries) require no more than a few days of an opioid analgesic. Clinical guidelines on opioid prescribing for some acute pain conditions are available. (2.1)
- Initiate the dosing regimen for each patient individually, taking into account the patient’s underlying cause and severity of pain, prior analgesic treatment and response, and risk factors for addiction, abuse, and misuse. (2.1, 5.1)
- Respiratory depression can occur at any time during opioid therapy, especially when initiating and following dosage increases with tramadol hydrochloride and acetaminophen tablets. Consider this risk when selecting an initial dose and when making dose adjustments. (2.1, 5.2)
- Periodically reassess patients receiving tramadol hydrochloride and acetaminophen to evaluate the continued need for opioid analgesics to maintain pain control, for the signs or symptoms of adverse reactions, and for the development of addiction, abuse, or misuse. (2.1)
- Discuss opioid overdose reversal agents and options for acquiring them with the patient and/or caregiver, both when initiating and renewing treatment with tramadol hydrochloride and acetaminophen tablets, especially if the patient has additional risk factors for overdose, or close contacts at risk for exposure and overdose. (2.2, 5.1, 5.2, 5.3)
- Do not use with other acetaminophen- or tramadol-containing products. (2, 5.20)
- Severe Renal Impairment:Do not exceed 2 tablets every 12 hours. (2.4)
- Initiate treatment with in a dosing range of two tablets every 4 to 6 as needed for pain relief, and at the lowest dosage necessary to achieve adequate analgesia. Titrate the dosage based upon the individual patient’s response to their initial dose of tramadol hydrochloride and acetaminophen tablets; maximum of 8 tablets per day (2.3, 5)
- Do not rapidly reduce or abruptly discontinue tramadol hydrochloride and acetaminophen in a physically dependent patient because rapid reduction or abrupt discontinuation of opioid analgesics has resulted in serious withdrawal symptoms, uncontrolled pain, and suicide. (2.5, 5.21)

3 DOSAGE FORMS AND STRENGTHS

Tablets: tramadol hydrochloride 37.5 mg and acetaminophen 325 mg. (3)

4 CONTRAINDICATIONS

- Children younger than 12 years of age (4)
- Postoperative management in children younger than 18 years of age following tonsillectomy and/or adenoidectomy. (4)
- Significant respiratory depression. (4)
- Acute or severe bronchial asthma in an unmonitored setting or in absence of resuscitative equipment. (4)
- Known or suspected gastrointestinal obstruction, including paralytic ileus. (4)
- Previous hypersensitivity to tramadol hydrochloride, acetaminophen, any other component of this product, or opioids. (4)
- Concurrent use of monoamine oxidase inhibitors (MAOIs) or use of MAOIs within the last 14 days (4)

5 WARNINGS AND PRECAUTIONS

- Opioid-Induced Hyperalgesia and Allodynia:Opioid-Induced Hyperalgesia (OIH) occurs when an opioid analgesic paradoxically causes an increase in pain, or an increase in sensitivity to pain. If OIH is suspected, carefully consider appropriately decreasing the dose of the current opioid analgesic, or opioid rotation. (5.8)
- Serotonin Syndrome:May be life-threatening. Can occur with use of tramadol alone, with concomitant use of serotonergic drugs, with drugs that impair metabolism of serotonin or tramadol. (5.10)
- Risk of Seizure:Can occur at the recommended dose of tramadol. Concomitant use with other drugs may increase seizure risk. Risk may increase in patients with epilepsy, a history of seizures, and in patients with a recognized risk for seizures. (5.11)
- Risk of Suicide:Do not prescribe for suicidal or addiction-prone patients. (5.12)
- Life-Threatening Respiratory Depression in Patients with Chronic Pulmonary Disease or in Elderly, Cachectic, or Debilitated Patients:Regularly evaluate closely, particularly during initiation and titration. (5.13)
- Adrenal Insufficiency:If diagnosed, treat with physiologic replacement of corticosteroids, and wean patient off of the opioid. (5.14)
- Severe Hypotension:Regularly evaluate during dosage initiation and titration. Avoid use of tramadol hydrochloride and acetaminophen in patients with circulatory shock. (5.15)
- Risks of Use in Patients with Increased Intracranial Pressure, Brain Tumors, Head Injury, or Impaired Consciousness:Regularly evaluate for sedation and respiratory depression. Avoid use of tramadol hydrochloride and acetaminophen in patients with impaired consciousness or coma. (5.16)

6 ADVERSE REACTIONS

The most common incidence of treatment-emergent adverse events (≥3%) in patients from clinical trials were constipation, diarrhea, nausea, somnolence, anorexia, dizziness, and sweating increased. (6)

To report SUSPECTED ADVERSE REACTIONS, contact Micro Labs USA, Inc. at 1-855-839-8195 or FDA at 1-800-FDA-1088 or www.fda.gov/medwatch.

7 DRUG INTERACTIONS

- Mixed Agonist/Antagonist and Partial Agonist Opioid Analgesics: Avoid use with tramadol hydrochloride and acetaminophen because they may reduce analgesic effect of tramadol hydrochloride and acetaminophen or precipitate withdrawal symptoms. (7)

8 USE IN SPECIFIC POPULATIONS

- Pregnancy: May cause fetal harm. (8.1)
- Lactation: Breastfeeding not recommended. (8.2)

FULL PRESCRIBING INFORMATION

WARNING: SERIOUS AND LIFE-THREATENING RISKS FROM USE OF TRAMADOL HYDROCHLORIDE AND ACETAMINOPHEN TABLETS

Addiction, Abuse, and Misuse

Because the use of tramadol hydrochloride and acetaminophen tablets exposes patients and other users to the risks of opioid addiction, abuse, and misuse, which can lead to overdose and death, assess each patient’s risk prior to prescribing and reassess all patients regularly for the development of these behaviors and conditions [see Warnings and Precautions (5.1)].

Life-Threatening Respiratory Depression

Serious, life-threatening, or fatal respiratory depression may occur with use of tramadol hydrochloride and acetaminophen tablets, especially during initiation or following a dosage increase. To reduce the risk of respiratory depression, proper dosing and titration of tramadol hydrochloride and acetaminophen tablets are essential [see Warnings and Precautions (5.2)].

Accidental Ingestion

Accidental ingestion of even one dose of tramadol hydrochloride and acetaminophen tablets, especially by children, can result in a fatal overdose of tramadol [see Warnings and Precautions (5.2)] .

Risks from Concomitant Use with Benzodiazepines or Other CNS Depressants

Concomitant use of opioids with benzodiazepines or other central nervous system (CNS) depressants, including alcohol, may result in profound sedation, respiratory depression, coma, and death. Reserve concomitant prescribing oftramadol hydrochloride and acetaminophen tabletsand benzodiazepines or other CNS depressants for use in patients for whom alternative treatment options are inadequate [see Warnings and Precautions (5.3) and Drug Interactions (7)] .

Neonatal Opioid Withdrawal Syndrome (NOWS)

Advise pregnant women using opioids for an extended period of time of the risk of Neonatal Opioid Withdrawal Syndrome, which may be life-threatening if not recognized and treated. Ensure that managementby neonatology experts will be available at delivery [see Warnings and Precautions (5.4)].

Opioid Analgesic Risk Evaluation and Mitigation Strategy (REMS)

Healthcare providers are strongly encouraged to complete a REMS-compliant education program and to counsel patients and caregivers on serious risks, safe use, and the importance of reading the Medication Guide with each prescription [see Warnings and Precautions (5.5)] .

Ultra-Rapid Metabolism of Tramadol and Other Risk Factors for Life-Threatening Respiratory Depression in Children

Life-threatening respiratory depression and death have occurred in children who received tramadol. Some of the reported cases occurred following tonsillectomy and/or adenoidectomy, and in at least one case, the child had evidence of being an ultra-rapid metabolizer of tramadol due to a CYP2D6 polymorphism [see Warnings and Precautions (5.6)]. Tramadol hydrochloride and acetaminophen tablet is contraindicated in children younger than 12 years of age and in children younger than 18 years of age following tonsillectomy and/or adenoidectomy [see Contraindications (4)]. Avoid the use of tramadol hydrochloride and acetaminophen tablets in adolescents 12 to 18 years of age who have other risk factors that may increase their sensitivity to the respiratory depressant effects of tramadol [see Warnings and Precautions (5.6)].

Interactions with Drugs Affecting Cytochrome P450 Isoenzymes

The effects of concomitant use or discontinuation of cytochrome P450 3A4 inducers, 3A4 inhibitors, or 2D6 inhibitors with tramadol are complex. Use of cytochrome P450 3A4 inducers, 3A4 inhibitors, or 2D6 inhibitors with tramadol hydrochloride and acetaminophen tablets requires careful consideration of the effects on the parent drug, tramadol, and the active metabolite, M1 [see Warnings and Precautions (5.7), Drug Interactions (7)].

Hepatotoxicity

Tramadol hydrochloride and acetaminophen tablet contains tramadol hydrochloride and acetaminophen. Acetaminophen has been associated with cases of acute liver failure, at times resulting in liver transplant and death. Most of the cases of liver injury are associated with the use of acetaminophen at doses that exceed 4,000 milligrams per day, and often involve more than one acetaminophen-containing product [see Warnings and Precautions (5.9)].

1 INDICATIONS AND USAGE

Tramadol hydrochloride and acetaminophen tablets are indicated for the management of acute pain severe enough to require an opioid analgesic and for which alternative treatments are inadequate.

Limitations of Use

Tramadol hydrochloride and acetaminophen tablets are indicated for short-term use of five days or less.

- Because of the risks of addiction, abuse, misuse, overdose, and death, which can occur at any dosage or duration and persist over the course of therapy [see Warning and Precautions (5.1)] , reserve opioid analgesics, including tramadol hydrochloride and acetaminophen, for use in patients for whom alternative treatment options are ineffective, not tolerated, or would be otherwise inadequate to provide sufficient management of pain.

2 DOSAGE AND ADMINISTRATION

2.1 Important Dosage and Administration Instructions

• Tramadol hydrochloride and acetaminophen is not approved for use for more than 5 days.
• Do not exceed the recommended dose of tramadol hydrochloride and acetaminophen. Do not co-administer tramadol hydrochloride and acetaminophen tablets with other tramadol or acetaminophen containing products [see Warnings and Precautions (5.20)].
• Tramadol hydrochloride and acetaminophen should be prescribed only by healthcare professionals who are knowledgeable about the use of opioids and how to mitigate the associated risks.
• Use the lowest effective dosage for the shortest duration of time consistent with individual patient treatment goals [see Warnings and Precautions (5)].
• Because the risk of overdose increases as opioid doses increase, reserve titration to higher doses of tramadol hydrochloride and acetaminophen for patients in whom lower doses are insufficiently effective and in whom the expected benefits of using a higher dose opioid clearly outweigh the substantial risks.
• Many acute pain conditions (e.g., the pain that occurs with a number of surgical procedures or acute musculoskeletal injuries) require no more than a few days of an opioid analgesic. Clinical guidelines on opioid prescribing for some acute pain conditions are available.
• There is variability in the opioid analgesic dose and duration needed to adequately manage pain due both to the cause of pain and to individual patient factors. Initiate the dosing regimen for each patient individually, taking into account the patient’s underlying cause and severity of pain, prior analgesic treatment and response, and risk factors for addiction, abuse, and misuse [see Warnings and Precautions (5.1)].
• Respiratory depression can occur at any time during opioid therapy, especially when initiating and following dosage increases with tramadol hydrochloride and acetaminophen. Consider this risk when selecting an initial dose and when making dose adjustments [see Warnings and Precautions (5.2)].

2.2 Patient Access to an Opioid Overdose Reversal Agent for the Emergency Treatment of Opioid Overdose

Inform patients and caregivers about opioid overdose reversal agents (e.g., naloxone, nalmefene). Discuss the importance of having access to an opioid overdose reversal agent, especially if the patient has risk factors for overdose (e.g., concomitant use of CNS depressants, a history of opioid use disorder, or prior opioid overdose) or if there are household members (including children) or other close contacts at risk for accidental ingestion or opioid overdose. The presence of risk factors for overdose should not prevent the management of pain in any patient [see Warnings and Precautions (5.1, 5.2, 5.3)] .

Discuss the options for obtaining an opioid overdose reversal agent (e.g., prescription, over-the-counter, or as part of a community-based program) [see Warnings and Precautions (5.2)] .

There are important differences among the opioid overdose reversal agents, such as route of administration, product strength, approved patient age range, and pharmacokinetics. Be familiar with these differences, as outlined in the approved labeling for those products, prior to recommending or prescribing such an agent.

2.3 Initial Dosage

Initiate treatment with tramadol hydrochloride and acetaminophen tablet is 2 tablets every 4 to 6 hours as needed for pain relief, up to a maximum of 8 tablets per day, and at the lowest dosage necessary to achieve adequate analgesia. Titrate the dose based upon the individual patient’s response to their initial dose of tramadol hydrochloride and acetaminophen.

2.4 Dosage Modification in Patients with Renal Impairment

In patients with creatinine clearances of less than 30 mL/min, do not exceed 2 tablets every 12 hours.

2.5 Safe Reduction or Discontinuation of Tramadol Hydrochloride and Acetaminophen Tablets

Do not rapidly reduce or abruptly discontinue tramadol hydrochloride and acetaminophen in patients who may be physically dependent on opioids. Rapid reduction or abrupt discontinuation of opioid analgesics in patients who are physically dependent on opioids has resulted in serious withdrawal symptoms, uncontrolled pain, and suicide. Rapid reduction or abrupt discontinuation has also been associated with attempts to find other sources of opioid analgesics, which may be confused with drug-seeking for abuse. Patients may also attempt to treat their pain or withdrawal symptoms with illicit opioids, such as heroin, and other substances.

When a decision has been made to decrease the dose or discontinue therapy in an opioid-dependent patient taking tramadol hydrochloride and acetaminophen, there are a variety of factors that should be considered, including the total daily dose of opioid (including tramadol hydrochloride and acetaminophen) the patient has been taking, the duration of treatment, the type of pain being treated, and the physical and psychological attributes of the patient. It is important to ensure ongoing care of the patient and to agree on an appropriate tapering schedule and follow-up plan so that patient and provider goals and expectations are clear and realistic. When opioid analgesics are being discontinued due to a suspected substance use disorder, evaluate and treat the patient, or refer for evaluation and treatment of the substance use disorder. Treatment should include evidence-based approaches, such as medication assisted treatment of opioid use disorder. Complex patients with comorbid pain and substance use disorders may benefit from referral to a specialist.
There are no standard opioid tapering schedules that are suitable for all patients. Good clinical practice dictates a patient-specific plan to taper the dose of the opioid gradually. For patients on opioids who are physically opioid-dependent, initiate the taper by a small enough increment (e.g., no greater than 10% to 25% of the total daily dose) to avoid withdrawal symptoms, and use a gradual downward taper. Patients who have been taking opioids for briefer periods of time may tolerate a more rapid taper.
It may be necessary to provide the patient with lower dosage strengths to accomplish a successful taper. Reassess the patient frequently to manage pain and withdrawal symptoms, should they emerge. Common withdrawal symptoms include restlessness, lacrimation, rhinorrhea, yawning, perspiration, chills, myalgia, and mydriasis. Other signs and symptoms also may develop, including irritability, anxiety, backache, joint pain, weakness, abdominal cramps, insomnia, nausea, anorexia, vomiting, diarrhea, or increased blood pressure, respiratory rate, or heart rate. If withdrawal symptoms arise, it may be necessary to pause the taper for a period of time or raise the dose of the opioid analgesic to the previous dose, and then proceed with a slower taper. In addition, evaluate patients for any changes in mood, emergence of suicidal thoughts, or use of other substances.
When managing patients taking opioid analgesics, particularly those who have been treated for an extended period of time, and/or with high doses for chronic pain, ensure that a multimodal approach to pain management, including mental health support (if needed), is in place prior to initiating an opioid analgesic taper. A multimodal approach to pain management may optimize the treatment of chronic pain, as well as assist with the successful tapering of the opioid analgesic [see Warnings and Precautions (5.21), Drug Abuse and Dependence (9.2)].

3 DOSAGE FORMS AND STRENGTHS

Tramadol hydrochloride and acetaminophen tablets USP, 37.5 mg/325 mg, are light yellow, oblong-shaped, biconvex, film-coated tablets debossed with “I 03” on one side and plain on the other side.

4 CONTRAINDICATIONS

Tramadol hydrochloride and acetaminophen is contraindicated for:

- all children younger than 12 years of age [see Warnings and Precautions (5.6)]
- post-operative management in children younger than 18 years of age following tonsillectomy and/or adenoidectomy [see Warnings and Precautions (5.6)] .

Tramadol hydrochloride and acetaminophen is also contraindicated in patients with:

- Significant respiratory depression [see Warnings and Precautions (5.2)] .
- Acute or severe bronchial asthma in an unmonitored setting or in the absence of resuscitative equipment [see Warnings and Precautions (5.14)] .
- Patients with known or suspected gastrointestinal obstruction, including paralytic ileus [see Warnings and Precautions (5.18)] .
- Previous hypersensitivity to tramadol, acetaminophen, any other component of this product, or opioids [see Warnings and Precautions (5.19)].

- Concurrent use of monoamine oxidase inhibitors (MAOIs) or use within the last 14 days [see Drug Interactions (7)].

5 WARNINGS AND PRECAUTIONS

5.1 Addiction, Abuse and Misuse

Tramadol hydrochloride and acetaminophen tablets contains tramadol, a Schedule IV controlled substance. As an opioid, tramadol hydrochloride and acetaminophen tablets exposes users to the risks of addiction, abuse, and misuse [see Drug Abuse and Dependence (9)] .

Although the risk of addiction in any individual is unknown, it can occur in patients appropriately prescribed tramadol hydrochloride and acetaminophen tablets. Addiction can occur at recommended doses and if the drug is misused or abused. The risk of opioid-related overdose or overdose-related death is increased with higher opioid doses, and this risk persists over the course of therapy. In postmarketing studies, addiction, abuse, misuse, and fatal and non-fatal opioid overdose were observed in patients with long-term opioid use [see Adverse Reactions (6.2)] .

Assess each patient’s risk for opioid addiction, abuse, or misuse prior to prescribing tramadol hydrochloride and acetaminophen, and reassess all patients receiving tramadol hydrochloride and acetaminophen for the development of these behaviors and conditions. Risks are increased in patients with a personal or family history of substance abuse (including drug or alcohol abuse or addiction) or mental illness (e.g., major depression). The potential for these risks should not, however, prevent the proper management of pain in any given patient. Patients at increased risk may be prescribed opioids such as tramadol hydrochloride and acetaminophen, but use in such patients necessitates intensive counseling about the risks and proper use of tramadol hydrochloride and acetaminophen along with frequent reevaluation for signs of addiction, abuse, and misuse. Consider recommending or prescribing an opioid overdose reversal agent [see Dosage and Administration (2.2), Warnings and Precautions (5.2)] .

Opioids are sought for nonmedical use and are subject to diversion from legitimate prescribed use. Consider these risks when prescribing or dispensing tramadol hydrochloride and acetaminophen tablets. Strategies to reduce these risks include prescribing the drug in the smallest appropriate quantity and advising the patient on careful storage of the drug during the course of treatment and proper disposal of unused drug. Contact local state professional licensing board or state-controlled substances authority for information on how to prevent and detect abuse or diversion of this product.

5.2 Life-Threatening Respiratory Depression

Serious, life-threatening, or fatal respiratory depression has been reported with the use of opioids, even when used as recommended. Respiratory depression, if not immediately recognized and treated, may lead to respiratory arrest and death. Management of respiratory depression may include close observation, supportive measures, and use of opioid overdose reversal agents, depending on the patient’s clinical status [see Overdosage (10)] . Carbon dioxide (CO2) retention from opioid-induced respiratory depression can exacerbate the sedating effects of opioids.

While serious, life-threatening, or fatal respiratory depression can occur at any time during the use of tramadol hydrochloride and acetaminophen, the risk is greatest during the initiation of therapy or following a dosage increase.

To reduce the risk of respiratory depression, proper dosing and titration of tramadol hydrochloride and acetaminophen are essential [see Dosage and Administration (2)]. Overestimating the tramadol hydrochloride and acetaminophen dosage when converting patients from another opioid product can result in a fatal overdose with the first dose.

Accidental ingestion of even one dose of tramadol hydrochloride and acetaminophen, especially by children, can result in respiratory depression and death due to an overdose of tramadol.

Educate patients and caregivers on how to recognize respiratory depression and emphasize the importance of calling 911 or getting emergency medical help right away in the event of a known or suspected overdose [see Patient Counseling Information (17)].

Opioids can cause sleep-related breathing disorders including central sleep apnea (CSA) and sleep-related hypoxemia. Opioid use increases the risk of CSA in a dose-dependent fashion. In patients who present with CSA, consider decreasing the opioid dosage using best practices for opioid taper [see Dosage and Administration (2.5)].

Patient Access to an Opioid Overdose Reversal Agent for the Emergency Treatment of Opioid Overdose

Inform patients and caregivers about opioid overdose reversal agents (e.g., naloxone, nalmefene). Discuss the importance of having access to an opioid overdose reversal agent, especially if the patient has risk factors for overdose (e.g., concomitant use of CNS depressants, a history of opioid use disorder, or prior opioid overdose) or if there are household members (including children) or other close contacts at risk for accidental ingestion or opioid overdose. The presence of risk factors for overdose should not prevent the management of pain in any patient [see Warnings and Precautions (5.1, 5.3)] .

Discuss the options for obtaining an opioid overdose reversal agent (e.g., prescription, over-the-counter, or as part of a community-based program).

There are important differences among the opioid overdose reversal agents, such as route of administration, product strength, approved patient age range, and pharmacokinetics. Be familiar with these differences, as outlined in the approved labeling for those products, prior to recommending or prescribing such an agent.

Educate patients and caregivers on how to recognize respiratory depression, and how to use an opioid overdose reversal agent for the emergency treatment of opioid overdose. Emphasize the importance of calling 911 or getting emergency medical help, even if an opioid overdose reversal agent is administered [see Dosage and Administration (2.2), Warnings and Precautions (5.1, 5.3), Overdosage (10)].

5.3 Risks from Concomitant Use with Benzodiazepines or Other CNS Depressants

Profound sedation, respiratory depression, coma, and death may result from the concomitant use of tramadol hydrochloride and acetaminophen tablets with benzodiazepines and/or other CNS depressants, including alcohol (e.g., non-benzodiazepine sedatives/hypnotics, anxiolytics, tranquilizers, muscle relaxants, general anesthetics, antipsychotics, gabapentinoids [gabapentin or pregabalin], and other opioids). Because of these risks, reserve concomitant prescribing of these drugs for use in patients for whom alternative treatment options are inadequate.

Observational studies have demonstrated that concomitant use of opioid analgesics and benzodiazepines increases the risk of drug-related mortality compared to use of opioid analgesics alone. Because of similar pharmacological properties, it is reasonable to expect similar risk with the concomitant use of other CNS depressant drugs with opioid analgesics [see Drug Interactions (7)].

If the decision is made to prescribe a benzodiazepine or other CNS depressant concomitantly with an opioid analgesic, prescribe the lowest effective dosages and minimum durations of concomitant use. In patients already receiving an opioid analgesic, prescribe a lower initial dose of the benzodiazepine or other CNS depressant than indicated in the absence of an opioid, and titrate based on clinical response. If an opioid analgesic is initiated in a patient already taking a benzodiazepine or other CNS depressant, prescribe a lower initial dose of the opioid analgesic, and titrate based on clinical response. Inform patients and caregivers of this potential interaction and educate them on the signs and symptoms of respiratory depression (including sedation).

If concomitant use is warranted, consider recommending or prescribing an opioid overdose reversal agent [see Dosage and Administration (2.2), Warnings and Precautions (5.2), Overdosage (10)].

Advise both patients and caregivers about the risks of respiratory depression and sedation when tramadol hydrochloride and acetaminophen tablets are used with benzodiazepines or other CNS depressants (including alcohol and illicit drugs). Advise patients not to drive or operate heavy machinery until the effects of concomitant use of the benzodiazepine or other CNS depressant have been determined. Screen patients for risk of substance use disorders, including opioid abuse and misuse, and warn them of the risk for overdose and death associated with the use of additional CNS depressants including alcohol and illicit drugs [see Drug Interactions (7), Patient Counseling Information (17)].

5.4 Neonatal Opioid Withdrawal Syndrome

Use of tramadol hydrochloride and acetaminophen for an extended period of time during pregnancy can result in withdrawal in the neonate. Neonatal opioid withdrawal syndrome, unlike opioid withdrawal syndrome in adults, may be life-threatening if not recognized and treated, and requires management according to protocols developed by neonatology experts. Observe newborns for signs of neonatal opioid withdrawal syndrome and manage accordingly. Advise pregnant women using opioids for an extended period of time of the risk of neonatal opioid withdrawal syndrome and ensure that appropriate treatment will be available [see Use in Specific Populations (8.1) and Patient Counseling Information (17)].

5.5 Opioid Analgesic Risk Evaluation and Mitigation Strategy (REMS)

To ensure that the benefits of opioid analgesics outweigh the risks of addiction, abuse, and misuse, the Food and Drug Administration (FDA) has required a Risk Evaluation and Mitigation Strategy (REMS) for these products. Under the requirements of the REMS, drug companies with approved opioid analgesic products must make REMS-compliant education programs available to healthcare providers. Healthcare providers are strongly encouraged to do all of the following:

- Complete a REMS-compliant education programoffered by an accredited provider of continuing education (CE) or another education program that includes all the elements of the FDA Education Blueprint for Health Care Providers Involved in the Management or Support of Patients with Pain.
- Discuss the safe use, serious risks, and proper storage and disposal of opioid analgesics with patients and/or their caregivers every time these medicines are prescribed. The Patient Counseling Guide (PCG) can be obtained at this link: www.fda.gov/OpioidAnalgesicREMSPCG.
- Emphasize to patients and their caregivers the importance of reading the Medication Guide that they will receive from their pharmacist every time an opioid analgesic is dispensed to them.
- Consider using other tools to improve patient, household, and community safety, such as patient-prescriber agreements that reinforce patient-prescriber responsibilities.

To obtain further information on the opioid analgesic REMS and for a list of accredited REMS CME/CE, call 1-800-503-0784, or log on to www.opioidanalgesicrems.com.

The FDA Blueprint can be found at www.fda.gov/OpioidAnalgesicREMSBlueprint.

5.6 Ultra-Rapid Metabolism of Tramadol and Other Risk Factors for Life-threatening Respiratory Depression in Children

Life-threatening respiratory depression and death have occurred in children who received tramadol. Tramadol and codeine are subject to variability in metabolism based upon CYP2D6 genotype (described below), which can lead to increased exposure to an active metabolite. Based upon postmarketing reports with tramadol or with codeine, children younger than 12 years of age may be more susceptible to the respiratory depressant effects of tramadol. Furthermore, children with obstructive sleep apnea who are treated with opioids for post-tonsillectomy and/or adenoidectomy pain may be particularly sensitive to their respiratory depressant effect. Because of the risk of life-threatening respiratory depression and death:

- Tramadol hydrochloride and acetaminophen is contraindicated for all children younger than 12 years of age [see Contraindications (4)] .
- Tramadol hydrochloride and acetaminophen is contraindicated for postoperative management in pediatric patients younger than 18 years of age following tonsillectomy and/or adenoidectomy [see Contraindications (4)] .
- Avoid the use of tramadol hydrochloride and acetaminophen in adolescents 12 to 18 years of age who have other risk factors that may increase their sensitivity to the respiratory depressant effects of tramadol unless the benefits outweigh the risks. Risk factors include conditions associated with hypoventilation such as postoperative status, obstructive sleep apnea, obesity, severe pulmonary disease, neuromuscular disease, and concomitant use of other medications that cause respiratory depression.
- As with adults, when prescribing opioids for adolescents, healthcare providers should choose the lowest effective dose for the shortest period of time and inform patients and caregivers about these risks and the signs of opioid overdose [see Use in Specific Populations (8.4), Overdosage (10)] .

Nursing Mothers

Tramadol is subject to the same polymorphic metabolism as codeine, with ultra-rapid metabolizers of CYP2D6 substrates being potentially exposed to life-threatening levels of O-desmethyl tramadol (M1). At least one death was reported in a nursing infant who was exposed to high levels of morphine in breast milk because the mother was an ultra-rapid metabolizer of codeine. A baby nursing from an ultra-rapid metabolizer mother taking tramadol hydrochloride and acetaminophen could potentially be exposed to high levels of M1, and experience life-threatening respiratory depression. For this reason, breastfeeding is not recommended during treatment with tramadol hydrochloride and acetaminophen [see Use in Specific Populations (8.2)] .

CYP2D6 Genetic Variability: Ultra-rapid metabolizer

Some individuals may be ultra-rapid metabolizers because of a specific CYP2D6 genotype (gene duplications denoted as *1/*1xN or *1/*2xN). The prevalence of this CYP2D6 phenotype varies widely and has been estimated at 1 to 10% for Whites (European, North American), 3 to 4% for Blacks (African Americans), 1 to 2% for East Asians (Chinese, Japanese, Korean), and may be greater than 10% in certain racial/ethnic groups (i.e., Oceanian, Northern African, Middle Eastern, Ashkenazi Jews, Puerto Rican). These individuals convert tramadol into its active metabolite, O-desmethyltramadol (M1), more rapidly and completely than other people. This rapid conversion results in higher than expected serum M1 levels. Even at labeled dosage regimens, individuals who are ultra-rapid metabolizers may have life-threatening or fatal respiratory depression or experience signs of overdose (such as extreme sleepiness, confusion, or shallow breathing) [see Overdosage (10)] . Therefore, individuals who are ultra-rapid metabolizers should not use tramadol hydrochloride and acetaminophen.

5.7 Risks of Interactions with Drugs Affecting Cytochrome P450 Isoenzymes

The effects of concomitant use or discontinuation of cytochrome P450 3A4 inducers, 3A4 inhibitors, or 2D6 inhibitors on levels of tramadol and M1 from tramadol hydrochloride and acetaminophen are complex. Use of cytochrome P450 3A4 inducers, 3A4 inhibitors, or 2D6 inhibitors with tramadol hydrochloride and acetaminophen requires careful consideration of the effects on the parent drug, tramadol, which is a weak serotonin and norepinephrine reuptake inhibitor and µ-opioid agonist, and the active metabolite, M1, which is more potent than tramadol in µ-opioid receptor binding [see Drug Interactions (7)] .

Risks of Concomitant Use or Discontinuation of Cytochrome P450 2D6 Inhibitors

The concomitant use of tramadol hydrochloride and acetaminophen tablets with all cytochrome P450 2D6 inhibitors (e.g., amiodarone, quinidine) may result in an increase in tramadol plasma levels and a decrease in the levels of the active metabolite, M1. A decrease in M1 exposure in patients who have developed physical dependence to tramadol, may result in signs and symptoms of opioid withdrawal and reduced efficacy. The effect of increased tramadol levels may be an increased risk for serious adverse events including seizures and serotonin syndrome.

Discontinuation of a concomitantly used cytochrome P450 2D6 inhibitor may result in a decrease in tramadol plasma levels and an increase in active metabolite M1 levels, which could increase or prolong adverse reactions related to opioid toxicity and may cause potentially fatal respiratory depression.

Evaluate patients receiving tramadol hydrochloride and acetaminophen tablets and any CYP2D6 inhibitor at frequent intervals for the risk of serious adverse events including seizures and serotonin syndrome, signs and symptoms that may reflect opioid toxicity, and opioid withdrawal when tramadol hydrochloride and acetaminophen tablets are used in conjunction with inhibitors of CYP2D6 [see Drug Interactions (7)] .

Cytochrome P450 3A4 Interaction

The concomitant use of tramadol hydrochloride and acetaminophen tablets with cytochrome P450 3A4 inhibitors, such as macrolide antibiotics (e.g., erythromycin), azole-antifungal agents (e.g., ketoconazole), and protease inhibitors (e.g., ritonavir) or discontinuation of a cytochrome P450 3A4 inducer such as rifampin, carbamazepine, and phenytoin, may result in an increase in tramadol plasma concentrations, which could increase or prolong adverse reactions, increase the risk for serious adverse events including seizures and serotonin syndrome, and may cause potentially fatal respiratory depression.

The concomitant use of tramadol hydrochloride and acetaminophen tablets with all cytochrome P450 3A4 inducers or discontinuation of a cytochrome P450 3A4 inhibitor may result in lower tramadol levels. This may be associated with a decrease in efficacy, and in some patients, may result in signs and symptoms of opioid withdrawal.

Evaluate patients receiving tramadol hydrochloride and acetaminophen tablets and any CYP3A4 inhibitor or inducer at frequent intervals for the risk for serious adverse events including seizures and serotonin syndrome, signs and symptoms that may reflect opioid toxicity and opioid withdrawal when tramadol hydrochloride and acetaminophen tablets are used in conjunction with inhibitors and inducers of CYP3A4 [see Drug Interactions (7)] .

5.8 Opioid-Induced Hyperalgesia and Allodynia

Opioid-Induced Hyperalgesia (OIH) occurs when an opioid analgesic paradoxically causes an increase in pain, or an increase in sensitivity to pain. This condition differs from tolerance, which is the need for increasing doses of opioids to maintain a defined effect [see Dependence (9.2)] . Symptoms of OIH include (but may not be limited to) increased levels of pain upon opioid dosage increase, decreased levels of pain upon opioid dosage decrease, or pain from ordinarily non-painful stimuli (allodynia). These symptoms may suggest OIH only if there is no evidence of underlying disease progression, opioid tolerance, opioid withdrawal, or addictive behavior.

Cases of OIH have been reported, both with short-term and longer-term use of opioid analgesics. Though the mechanism of OIH is not fully understood, multiple biochemical pathways have been implicated. Medical literature suggests a strong biologic plausibility between opioid analgesics and OIH and allodynia. If a patient is suspected to be experiencing OIH, carefully consider appropriately decreasing the dose of the current opioid analgesic, or opioid rotation (safely switching the patient to a different opioid moiety) [see Dosage and Administration (2.5); Warnings and Precautions (5.21)] .

5.9 Hepatotoxicity

Tramadol hydrochloride and acetaminophen tablets contains tramadol hydrochloride and acetaminophen. Acetaminophen has been associated with cases of acute liver failure, at times resulting in liver transplant and death. Most of the cases of liver injury are associated with the use of acetaminophen at doses that exceed 4,000 milligrams per day, and often involve more than one acetaminophen-containing product. The excessive intake of acetaminophen may be intentional to cause self-harm or unintentional as patients attempt to obtain more pain relief or unknowingly take other acetaminophen-containing products.

The risk of acute liver failure is higher in individuals with underlying liver disease and in individuals who ingest alcohol while taking acetaminophen.

Instruct patients to look for acetaminophen or APAP on package labels and not to use more than one product that contains acetaminophen. Instruct patients to seek medical attention immediately upon ingestion of more than 4,000 milligrams of acetaminophen per day, even if they feel well.

5.10 Serotonin Syndrome Risk

Cases of serotonin syndrome, a potentially life-threatening condition, have been reported with the use of tramadol, including tramadol hydrochloride and acetaminophen tablets, during concomitant use with serotonergic drugs.

Serotonergic drugs include selective serotonin reuptake inhibitors (SSRIs), serotonin and norepinephrine reuptake inhibitors (SNRIs), tricyclic antidepressants (TCAs), triptans, 5-HT3 receptor antagonists, drugs that affect the serotonergic neurotransmitter system (e.g., mirtazapine, trazodone, tramadol), certain muscle relaxants (i.e., cyclobenzaprine, metaxalone), and drugs that impair metabolism of serotonin (including MAO inhibitors, both those intended to treat psychiatric disorders and also others, such as linezolid and intravenous methylene blue) [see Drug Interactions (7)]. This may occur within the recommended dosage range.

Serotonin syndrome symptoms may include mental status changes (e.g., agitation, hallucinations, coma), autonomic instability (e.g., tachycardia, labile blood pressure, hyperthermia), neuromuscular aberrations (e.g., hyperreflexia, incoordination, rigidity), and/or gastrointestinal symptoms (e.g., nausea, vomiting, diarrhea). The onset of symptoms generally occurs within several hours to a few days of concomitant use, but may occur later than that. Discontinue tramadol hydrochloride and acetaminophen if serotonin syndrome is suspected.

5.11 Increased Risk of Seizures

Seizures have been reported in patients receiving tramadol within the recommended dosage range. Spontaneous postmarketing reports indicate that seizure risk is increased with doses of tramadol above the recommended range.

Concomitant use of tramadol increases the seizure risk in patients taking: [see Drug Interactions (7)] .

- Selective serotonin re-uptake inhibitors (SSRIs) and Serotonin-norepinephrine re-uptake inhibitors (SNRIs) antidepressants or anorectics,
- Tricyclic antidepressants (TCAs), and other tricyclic compounds (e.g., cyclobenzaprine, promethazine, etc.),
- Other opioids,
- MAO inhibitors [see Warnings and Precautions (5.10), Drug Interactions (7)]
- Neuroleptics, or
- Other drugs that reduce the seizure threshold.

Risk of seizures may also increase in patients with epilepsy, those with a history of seizures, or in patients with a recognized risk for seizure (such as head trauma, metabolic disorders, alcohol and drug withdrawal, CNS infections).

In tramadol overdose, administration of an opioid overdose reversal agent (e.g., naloxone or nalmefene) may increase the risk of seizure.

5.12 Suicide Risk

- Do not prescribe tramadol hydrochloride and acetaminophen for patients who are suicidal or addiction-prone. Consideration should be given to the use of non-narcotic analgesics in patients who are suicidal or depressed [see Drug Abuse and Dependence (9)].
- Prescribe tramadol hydrochloride and acetaminophen with caution for patients with a history of misuse and/or are currently taking CNS-active drugs including tranquilizers, or antidepressant drugs, or alcohol in excess, and patients who suffer from emotional disturbance or depression [see Drug Interactions (7)] .
- Inform patients not to exceed the recommended dose and to limit their intake of alcohol [see Dosage and Administration (2), Warnings and Precautions (5.3, 5.9)] .

5.13 Life-Threatening Respiratory Depression in Patients with Chronic Pulmonary Disease or in Elderly, Cachectic, or Debilitated Patients

The use of tramadol hydrochloride and acetaminophen in patients with acute or severe bronchial asthma in an unmonitored setting or in the absence of resuscitative equipment is contraindicated [see Contraindications (4)] .

Patients with Chronic Pulmonary Disease: Tramadol hydrochloride and acetaminophen-treated patients with significant chronic obstructive pulmonary disease or cor pulmonale, and those with a substantially decreased respiratory reserve, hypoxia, hypercapnia, or pre-existing respiratory depression are at increased risk of decreased respiratory drive including apnea, even at recommended dosages of tramadol hydrochloride and acetaminophen [see Warnings and Precautions (5.2)] .

Elderly, Cachectic, or Debilitated Patients: Life-threatening respiratory depression is more likely to occur in elderly, cachectic, or debilitated patients because they may have altered pharmacokinetics, or altered clearance, compared to younger, healthier patients [see Warnings and Precautions (5.2)] .

Regularly evaluate patients, particularly when initiating and titrating tramadol hydrochloride and acetaminophen and when tramadol hydrochloride and acetaminophen is given concomitantly with other drugs that depress respiration [see Warnings and Precautions (5.2), Drug Interactions (7)] . Alternatively, consider the use of non-opioid analgesics in these patients.

5.14 Adrenal Insufficiency

Cases of adrenal insufficiency have been reported with opioid use, more often following greater than one month of use. Presentation of adrenal insufficiency may include non-specific symptoms and signs including nausea, vomiting, anorexia, fatigue, weakness, dizziness, and low blood pressure. If adrenal insufficiency is suspected, confirm the diagnosis with diagnostic testing as soon as possible. If adrenal insufficiency is diagnosed, treat with physiologic replacement doses of corticosteroids. Wean the patient off of the opioid to allow adrenal function to recover and continue corticosteroid treatment until adrenal function recovers. Other opioids may be tried as some cases reported use of a different opioid without recurrence of adrenal insufficiency. The information available does not identify any particular opioids as being more likely to be associated with adrenal insufficiency.

5.15 Severe Hypotension

Tramadol hydrochloride and acetaminophen may cause severe hypotension including orthostatic hypotension and syncope in ambulatory patients. There is increased risk in patients whose ability to maintain blood pressure has already been compromised by a reduced blood volume or concurrent administration of certain CNS depressant drugs (e.g., phenothiazines or general anesthetics) [see Drug Interactions (7)] . Regularly evaluate these patients for signs of hypotension after initiating or titrating the dosage of tramadol hydrochloride and acetaminophen. In patients with circulatory shock, tramadol hydrochloride and acetaminophen may cause vasodilation that can further reduce cardiac output and blood pressure. Avoid the use of tramadol hydrochloride and acetaminophen in patients with circulatory shock.

5.16 Risk of Use in Patients with Increased Intracranial Pressure, Brain Tumors, Head Injury, or Impaired Consciousness

In patients who may be susceptible to the intracranial effects of CO2retention (e.g., those with evidence of increased intracranial pressure or brain tumors), tramadol hydrochloride and acetaminophen may reduce respiratory drive, and the resultant CO2retention can further increase intracranial pressure. Regularly evaluate such patients for signs of sedation and respiratory depression, particularly when initiating therapy with tramadol hydrochloride and acetaminophen.

Opioids may also obscure the clinical course in a patient with a head injury. Avoid the use of tramadol hydrochloride and acetaminophen in patients with impaired consciousness or coma.

5.17 Serious Skin Reactions

Rarely, acetaminophen may cause serious skin reactions such as acute generalized exanthematous pustulosis (AGEP), Stevens-Johnson Syndrome (SJS), and toxic epidermal necrolysis (TEN), which can be fatal. Patients should be informed about the signs of serious skin reactions, and use of the drug should be discontinued at the first appearance of skin rash or any other sign of hypersensitivity.

5.18 Risk of Gastrointestinal Complications

Tramadol hydrochloride and acetaminophen tablets are contraindicated in patients with known or suspected gastrointestinal obstruction, including paralytic ileus [see Contraindications (4)] .

The tramadol in tramadol hydrochloride and acetaminophen tablets may cause spasm of the sphincter of Oddi. Opioids may cause increases in serum amylase. Regularly evaluate patients with biliary tract disease, including acute pancreatitis, for worsening symptoms.

Cases of opioid-induced esophageal dysfunction (OIED) have been reported in patients taking opioids. The risk of OIED may increase as the dose and/or duration of opioids increases. Regularly evaluate patients for signs and symptoms of OIED (e.g., dysphagia, regurgitation, non-cardiac chest pain) and, if necessary, adjust opioid therapy as clinically appropriate [see Clinical Pharmacology (12.2)] .

5.19 Anaphylaxis and Other Hypersensitivity Reactions

Serious and rarely fatal anaphylactic reactions have been reported in patients receiving therapy with tramadol. When these events do occur it is often following the first dose. Other reported allergic reactions include pruritus, hives, bronchospasm, angioedema, toxic epidermal necrolysis, and Stevens-Johnson syndrome. Patients with a history of anaphylactoid reactions to tramadol and other opioids may be at increased risk and therefore should not receive tramadol hydrochloride and acetaminophen. If anaphylaxis or other hypersensitivity occurs, stop administration of tramadol hydrochloride and acetaminophen immediately, discontinue tramadol hydrochloride and acetaminophen permanently, and do not rechallenge with any formulation of tramadol. Advise patients to seek immediate medical attention if they experience any symptoms of a hypersensitivity reaction [see Contraindications (4), Information for Patients (17)] .

There have been postmarketing reports of hypersensitivity and anaphylaxis associated with the use of acetaminophen. Clinical signs included swelling of the face, mouth, and throat, respiratory distress, urticaria, rash, pruritus, and vomiting. There were infrequent reports of life-threatening anaphylaxis requiring emergency medical attention. Instruct patients to discontinue tramadol hydrochloride and acetaminophen immediately and seek medical care if they experience these symptoms. Do not prescribe tramadol hydrochloride and acetaminophen for patients with acetaminophen allergy.

5.20 Increased Risk of Hepatotoxicity with Concomitant Use of Other Acetaminophen-containing Products

Due to the potential for acetaminophen hepatotoxicity at doses higher than the recommended dose, tramadol hydrochloride and acetaminophen should not be used concomitantly with other acetaminophen containing products.

5.21 Withdrawal

Do not rapidly reduce or abruptly discontinue tramadol hydrochloride and acetaminophen in a patient physically dependent on opioids. When discontinuing tramadol hydrochloride and acetaminophen in a physically dependent patient, gradually taper the dosage. Rapid tapering of tramadol and acetaminophen in a patient physically dependent on opioids may lead to a withdrawal syndrome and return of pain [see Dosage and Administration (2.5), Drug Abuse and Dependence (9.2)] .

Additionally, avoid the use of mixed agonist/antagonist (e.g., pentazocine, nalbuphine, and butorphanol) or partial agonist (e.g., buprenorphine) analgesics in patients who are receiving a full opioid agonist analgesic, including tramadol hydrochloride and acetaminophen. In these patients, mixed agonist/antagonist and partial agonist analgesics may reduce the analgesic effect and/or may precipitate withdrawal symptoms [see Drug Interactions (7)] .

5.22 Driving and Operating Machinery

Tramadol hydrochloride and acetaminophen may impair the mental or physical abilities needed to perform potentially hazardous activities such as driving a car or operating machinery. Warn patients not to drive or operate dangerous machinery unless they are tolerant to the effects of tramadol hydrochloride and acetaminophen and know how they will react to the medication [see Patient Counseling Information (17)] .

5.23 Hyponatremia

Hyponatremia (serum sodium < 135 mmol/L) has been reported with the use of tramadol, and many cases are severe (sodium level < 120 mmol/L). Most cases of hyponatremia occurred in females over the age of 65 and within the first week of therapy. In some reports, hyponatremia resulted from the syndrome of inappropriate antidiuretic hormone secretion (SIADH). Regularly evaluate patients for signs and symptoms of hyponatremia (e.g., confusion, disorientation), during treatment with tramadol hydrochloride and acetaminophen, especially during initiation of therapy. If signs and symptoms of hyponatremia are present, initiate appropriate treatment (e.g., fluid restriction) and discontinue tramadol hydrochloride and acetaminophen [see Dosage and Administration: Safe Reduction or Discontinuation of Tramadol Hydrochloride and Acetaminophen (2.5)].

5.24 Hypoglycemia

Cases of tramadol-associated hypoglycemia have been reported, some resulting in hospitalization. In most cases, patients had predisposing risk factors (e.g. diabetes). If hypoglycemia is suspected, monitor blood glucose levels and consider drug discontinuation as appropriate [see Dosage and Administration: Safe Reduction or Discontinuation of Tramadol Hydrochloride and Acetaminophen (2.5)] .

6 ADVERSE REACTIONS

The following serious adverse reactions are discussed, or described in greater detail, in other sections:

- Addiction, Abuse, and Misuse [see Warnings and Precautions (5.1)]
- Life-Threatening Respiratory Depression [see Warnings and Precautions (5.2)]
- Ultra-Rapid Metabolism of Tramadol and Other Risk Factors for Life-threatening Respiratory Depression in Children [see Warnings and Precautions (5.6)]
- Neonatal Opioid Withdrawal Syndrome [see Warnings and Precautions (5.4)]
- Hepatotoxicity [see Warnings and Precautions (5.9)]
- Interactions with Benzodiazepines or Other CNS Depressants [see Warnings and Precautions (5.3)]
- Serotonin Syndrome [see Warnings and Precautions (5.10)]
- Seizures [see Warnings and Precautions (5.11)]
- Suicide [see Warnings and Precautions (5.12)]
- Adrenal Insufficiency [see Warnings and Precautions (5.14)]
- Severe Hypotension [see Warnings and Precautions (5.15)]
- Gastrointestinal Adverse Reactions [see Warnings and Precautions (5.18)]
- Hypersensitivity Reactions [see Warnings and Precautions (5.19)]
- Withdrawal [see Warnings and Precautions (5.21)]
- Opioid-Induced Hyperalgesia and Allodynia [see Warnings and Precautions (5.8)] .

6.1 Clinical Trials Experience

Because clinical trials are conducted under widely varying conditions, adverse reaction rates observed in the clinical trials of a drug cannot be directly compared to rates in the clinical trials of another drug and may not reflect the rates observed in practice.

The most common incidence of treatment-emergent adverse events (≥3%) in subjects from clinical trials was constipation, diarrhea, nausea, somnolence, anorexia, dizziness, and sweating increased.

Table 1 shows the incidence rate of treatment-emergent adverse events reported in ≥2% of subjects over five days of tramadol hydrochloride and acetaminophen use in clinical trials (subjects took an average of at least 6 tablets per day).

Table 1: Incidence of Treatment-Emergent Adverse Events (≥2%)

Body System Preferred Term | Tramadol Hydrochloride and Acetaminophen (N=142) (%)
Gastrointestinal System Disorders
Constipation | 6
Diarrhea | 3
Nausea | 3
Dry Mouth | 2
Psychiatric Disorders
Somnolence | 6
Anorexia | 3
Insomnia | 2
Central & Peripheral Nervous System
Dizziness | 3
Skin and Appendages
Sweating Increased | 4
Pruritus | 2
Reproductive Disorders, Male*
Prostatic Disorder | 2

* Number of males = 62

Incidence at least 1%, causal relationship at least possible or greater:

The following lists adverse reactions that occurred with an incidence of at least 1% in single-dose or repeated-dose clinical trials of tramadol hydrochloride and acetaminophen.

Body as a Whole- Asthenia, fatigue, hot flushes

Central and Peripheral Nervous System- Dizziness, headache, tremor

Gastrointestinal System- Abdominal pain, constipation, diarrhea, dyspepsia, flatulence, dry mouth, nausea, vomiting

Psychiatric Disorders -Anorexia, anxiety, confusion, euphoria, insomnia, nervousness, somnolence

Skin and Appendages- Pruritus, rash, increased sweating

Selected adverse events occurring at less than 1%:

The following lists clinically relevant adverse reactions that occurred with an incidence of less than 1% in tramadol hydrochloride and acetaminophen clinical trials.

Body as a Whole- Chest pain, rigors, syncope, withdrawal syndrome

Cardiovascular Disorders -Hypertension, aggravated hypertension, hypotension

Central and Peripheral Nervous System- Ataxia, convulsions, hypertonia, migraine, aggravated migraine, involuntary muscle contractions, paresthesias, stupor, vertigo

Gastrointestinal System- Dysphagia, melena, tongue edema

Hearing and Vestibular Disorders- Tinnitus

Heart Rate and Rhythm Disorders -Arrhythmia, palpitation, tachycardia

Liver and Biliary System -Hepatic function abnormal

Metabolic and Nutritional Disorders -Weight decrease

Psychiatric Disorders- Amnesia, depersonalization, depression, drug abuse, emotional lability, hallucination, impotence, paroniria, abnormal thinking

Red Blood Cell Disorders- Anemia

Respiratory System -Dyspnea

Urinary System- Albuminuria, micturition disorder, oliguria, urinary retention

Vision Disorders -Abnormal vision

6.2 Postmarketing Experiences

The following adverse reactions have been identified during post-approval use of tramadol-containing products. Because these reactions are reported voluntarily from a population of uncertain size, it is not always possible to reliably estimate their frequency or establish a causal relationship to drug exposure.

Serotonin syndrome: Cases of serotonin syndrome, a potentially life-threatening condition, have been reported during concomitant use of opioids with serotonergic drugs.

Adrenal insufficiency: Cases of adrenal insufficiency have been reported with opioid use, more often following greater than one month of use.

Anaphylaxis: Anaphylaxis has been reported with ingredients contained in tramadol hydrochloride and acetaminophen tablets.

Androgen deficiency: Cases of androgen deficiency have occurred with use of opioids for an extended period of time [see Clinical Pharmacology (12.2)] .

Hyperalgesia and Allodynia:Cases of hyperalgesia and allodynia have been reported with opioid therapy of any duration [see Warnings and Precautions (5.8)].

QT prolongation/torsade de pointes:Cases of QT prolongation and/or torsade de pointes have been reported with tramadol use. Many of these cases were reported in patients taking another drug labeled for QT prolongation, in patients with a risk factor for QT prolongation (e.g., hypokalemia), or in the overdose setting.

Eye disorders- miosis, mydriasis

Metabolism and nutrition disorders -Hyponatremia: Cases of severe hyponatremia and/or SIADH have been reported in patients taking tramadol, most often in females over the age of 65, and within the first week of therapy [see Warnings and Precautions (5.23)].

Hypoglycemia: Cases of hypoglycemia have been reported in patients taking tramadol. Most reports were in patients with predisposing risk factors, including diabetes or renal insufficiency, or in elderly patients [see Warnings and Precautions (5.24)] .

Nervous system disorders- movement disorder, speech disorder

Psychiatric disorders- delirium

Other clinically significant adverse experiences previously reported with tramadol hydrochloride:

Other events which have been reported with the use of tramadol products and for which a causal association has not been determined include: vasodilation, orthostatic hypotension, myocardial ischemia, pulmonary edema, allergic reactions (including anaphylaxis and urticaria, Stevens-Johnson syndrome/TENS), cognitive dysfunction, difficulty concentrating, depression, suicidal tendency, hepatitis, liver failure, and gastrointestinal bleeding. Reported laboratory abnormalities included elevated creatinine and liver function tests. Serotonin syndrome (whose symptoms may include mental status change, hyperreflexia, fever, shivering, tremor, agitation, diaphoresis, seizures, and coma) has been reported with tramadol when used concomitantly with other serotonergic agents such as SSRIs and MAOIs.

Opioid-induced esophageal dysfunction (OIED): Cases of OIED have been reported in patients taking opioids and may occur more frequently in patients taking higher doses of opioids, and/or in patients taking opioids longer term [see Warnings and Precautions (5.18)] .

Adverse Reactions from Observational Studies

A prospective, observational cohort study estimated the risks of addiction, abuse, and misuse in patients initiating long-term use of Schedule II opioid analgesics between 2017 and 2021. Study participants included in one or more analyses had been enrolled in selected insurance plans or health systems for at least one year, were free of at least one outcome at baseline, completed a minimum number of follow-up assessments, and either: 1) filled multiple extended-release/long-acting opioid analgesic prescriptions during a 90-day period (n=978); or 2) filled any Schedule II opioid analgesic prescriptions covering at least 70 of 90 days (n=1,244). Those included also had no dispensing of the qualifying opioids in the previous 6 months.

Over 12 months:

- approximately 1% to 6% of participants across the two cohorts newly met criteria for addiction, as assessed with two validated interview-based measures of moderate-to-severe opioid use disorder based on Diagnostic and Statistical Manual of Mental Disorders, Fifth Edition (DSM-5) criteria, and
- approximately 9% and 22% of participants across the two cohorts newly met criteria for prescription opioid abuse and misuse [defined in Drug Abuse and Dependence (9.2)], respectively, as measured with a validated self-reported instrument.

A retrospective, observational cohort study estimated the risk of opioid-involved overdose or opioid overdose-related death in patients with new long-term use of Schedule II opioid analgesics from 2006 through 2016 (n=220,249). Included patients had been enrolled in either one of two commercial insurance programs, one managed care program, or one Medicaid program for at least 9 months. New long-term usewas defined as having Schedule II opioid analgesic prescriptions covering at least 70 days’ supply over the 3 months prior to study entry and none during the preceding 6 months. Patients were excluded if they had an opioid-involved overdose in the 9 months prior to study entry. Overdose was measured using a validated medical code-based algorithm with linkage to the National Death Index database. The 5-year cumulative incidence estimates for opioid-involved overdose or opioid overdose-related death ranged from approximately 1.5% to 4% across study sites, counting only the first event during follow-up. Approximately 17% of first opioid overdoses observed over the entire study period (5 to 11 years, depending on the study site) were fatal. Higher baseline opioid dose was the strongest and most consistent predictor of opioid-involved overdose or opioid overdose-related death. Study exclusion criteria may have selected patients at lower risk of overdose, and substantial loss to follow-up (approximately 80%) also may have biased estimates.

The risk estimates from the studies described above may not be generalizable to all patients receiving opioid analgesics, such as those with exposures shorter or longer than the duration evaluated in the studies.

7 DRUG INTERACTIONS

Table 2 includes clinically significant interactions with tramadol hydrochloride and acetaminophen.

Table 2: Clinically Significant Drug Interactions with Tramadol Hydrochloride and Acetaminophen Tablets

Inhibitors of CYP2D6
Clinical Impact: | The concomitant use of tramadol hydrochloride and acetaminophen tablets and CYP2D6 inhibitors may result in an increase in the plasma concentration of tramadol and a decrease in the plasma concentration of M1, particularly when an inhibitor is added after a stable dose of tramadol hydrochloride and acetaminophen is achieved. Since M1 is a more potent µ-opioid agonist, decreased M1 exposure could result in decreased therapeutic effects, and may result in signs and symptoms of opioid withdrawal in patients who had developed physical dependence to tramadol. Increased tramadol exposure can result in increased or prolonged therapeutic effects and increased risk for serious adverse events including seizures and serotonin syndrome. After stopping a CYP2D6 inhibitor, as the effects of the inhibitor decline, the tramadol plasma concentration will decrease and the M1 plasma concentration will increase which could increase or prolong therapeutic effects but also increase adverse reactions related to opioid toxicity, and may cause potentially fatal respiratory depression [see Clinical Pharmacology (12.3)] .
Intervention: | If concomitant use of a CYP2D6 inhibitor is necessary, evaluate patients at frequent intervals for adverse reactions including opioid withdrawal, seizures and serotonin syndrome. If a CYP2D6 inhibitor is discontinued, consider lowering tramadol hydrochloride and acetaminophen dosage until stable drug effects are achieved. Evaluate patients at frequent intervals for adverse events including respiratory depression and sedation.
Examples: | Quinidine, fluoxetine, paroxetine and bupropion
Inhibitors of CYP3A4
Clinical Impact: | The concomitant use of tramadol hydrochloride and acetaminophen tablets and CYP3A4 inhibitors can increase the plasma concentration of tramadol and may result in a greater amount of metabolism via CYP2D6 and greater levels of M1. Follow patients closely for increased risk of serious adverse events including seizures and serotonin syndrome, and adverse reactions related to opioid toxicity including potentially fatal respiratory depression, particularly when an inhibitor is added after a stable dose of tramadol hydrochloride and acetaminophen is achieved. After stopping a CYP3A4 inhibitor, as the effects of the inhibitor decline, the tramadol plasma concentration will decrease [see Clinical Pharmacology (12.3)] , resulting in decreased opioid efficacy and possibly signs and symptoms of opioid withdrawal in patients who had developed physical dependence to tramadol.
Intervention: | If concomitant use is necessary, consider dosage reduction of tramadol hydrochloride and acetaminophen until stable drug effects are achieved. Evaluate patients at frequent intervals for seizures and serotonin syndrome, and signs of respiratory depression and sedation at frequent intervals. If a CYP3A4 inhibitor is discontinued, consider increasing the tramadol hydrochloride and acetaminophen dosage until stable drug effects are achieved and evaluate patients for signs and symptoms of opioid withdrawal.
Examples: | Macrolide antibiotics (e.g., erythromycin), azole-antifungal agents (e.g. ketoconazole), protease inhibitors (e.g., ritonavir)
CYP3A4 Inducers
Clinical Impact: | The concomitant use of tramadol hydrochloride and acetaminophen tablets and CYP3A4 inducers can decrease the plasma concentration of tramadol [see Clinical Pharmacology (12.3)] , resulting in decreased efficacy or onset of a withdrawal syndrome in patients who have developed physical dependence to tramadol. After stopping a CYP3A4 inducer, as the effects of the inducer decline, the tramadol plasma concentration will increase [see Clinical Pharmacology (12.3)] , which could increase or prolong both the therapeutic effects and adverse reactions, and may cause serious respiratory depression, seizures and serotonin syndrome.
Intervention: | If concomitant use is necessary, consider increasing the tramadol hydrochloride and acetaminophen dosage until stable drug effects are achieved. Evaluate patients for signs of opioid withdrawal. If a CYP3A4 inducer is discontinued, consider tramadol hydrochloride and acetaminophen tablets dosage reduction and evaluate patients at frequent intervals for seizures and serotonin syndrome, and signs of respiratory depression and sedation. Patients taking carbamazepine, a CYP3A4 inducer, may have a significantly reduced analgesic effect of tramadol. Because carbamazepine increases tramadol metabolism and because of the seizure risk associated with tramadol, concomitant administration of tramadol hydrochloride and acetaminophen and carbamazepine is not recommended.
Examples: | Rifampin, carbamazepine, phenytoin
Benzodiazepines and Other Central Nervous System (CNS) Depressants
Clinical Impact: | Due to additive pharmacologic effect, the concomitant use of benzodiazepines or other CNS depressants, including alcohol, can increase the risk of hypotension, respiratory depression, profound sedation, coma, and death.
Intervention: | Reserve concomitantprescribing of these drugs for use in patients for whom alternative treatment options are inadequate. Limit dosages and durations to the minimum required. Inform patients and caregivers of this potential interaction and educate them on the signs and symptoms of respiratory depression (including sedation). If concomitant use is warranted, consider recommending or prescribing an opioid overdose reversal agent [see Dosage and Administration (2.2), Warnings and Precautions (5.1, 5.2, 5.3)] .
Examples: | Benzodiazepines and other sedatives/hypnotics, anxiolytics, tranquilizers, muscle relaxants, general anesthetics, antipsychotics, gabapentinoids (gabapentin or pregabalin), other opioids, alcohol.
Serotonergic Drugs
Clinical Impact: | The concomitant use of opioids with other drugs that affect the serotonergic neurotransmitter system has resulted in serotonin syndrome.
Intervention: | If concomitant use is warranted, frequently evaluate the patient, particularly during treatment initiation and dose adjustment. Discontinue tramadol hydrochloride and acetaminophen if serotonin syndrome is suspected.
Examples: | Selective serotonin reuptake inhibitors (SSRIs), serotonin and norepinephrine reuptake inhibitors (SNRIs), tricyclic antidepressants (TCAs), triptans, 5-HT3 receptor antagonists, drugs that affect the serotonin neurotransmitter system (e.g., mirtazapine, trazodone, tramadol), certain muscle relaxants (i.e., cyclobenzaprine, metaxalone), monoamine oxidase (MAO) inhibitors (those intended to treat psychiatric disorders and also others, such as linezolid and intravenous methylene blue).
Monoamine Oxidase Inhibitors (MAOIs)
Clinical Impact: | MAOI interactions with opioids may manifest as serotonin syndrome [see Warnings and Precautions (5.9)] or opioid toxicity (e.g., respiratory depression, coma) [see Warnings and Precautions (5.2)] .
Intervention: | Do not use tramadol hydrochloride and acetaminophen in patients taking MAOIs or within 14 days of stopping such treatment.
Examples: | phenelzine, tranylcypromine, linezolid
Mixed Agonist/Antagonist and Partial Agonist Opioid Analgesics
Clinical Impact: | May reduce the analgesic effect of tramadol hydrochloride and acetaminophen and/or precipitate withdrawal symptoms.
Intervention: | Avoid concomitant use.
Examples: | butorphanol, nalbuphine, pentazocine, buprenorphine
Muscle Relaxants
Clinical Impact: | Tramadol may enhance the neuromuscular blocking action of skeletal muscle relaxants and produce an increased degree of respiratory depression.
Intervention: | Monitor patients for signs of respiratory depression that may be greater than otherwise expected, decrease the dosage of tramadol hydrochloride and acetaminophen tablets and/or the muscle relaxant as necessary. Due to the risk of respiratory depression with concomitant use of skeletal musclerelaxants and opioids, consider recommending or prescribing an opioid overdose reversal agent [see Dosage and Administration (2.2), Warnings and Precautions (5.2, 5.3)] .
Examples | Cyclobenzaprine, metaxalone.
Diuretics
Clinical Impact: | Opioids can reduce the efficacy of diuretics by inducing the release of antidiuretic hormone.
Intervention: | Evaluate patients for signs of diminished diuresis and/or effects on blood pressure and increase the dosage of the diuretic as needed.
Anticholinergic Drugs
Clinical Impact: | The concomitant use of anticholinergic drugs may increase risk of urinary retention and/or severe constipation, which may lead to paralytic ileus.
Intervention: | Evaluate patients for signs of urinary retention or reduced gastric motility when tramadol hydrochloride and acetaminophen is used concomitantly with anticholinergic drugs.
Digoxin
Clinical Impact: | Postmarketing surveillance of tramadol has revealed rare reports of digoxin toxicity.
Intervention: | Evaluate patients at frequent intervals for signs of digoxin toxicity and adjust dosage of digoxin as needed.
Warfarin
Clinical Impact: | Postmarketing surveillance of tramadol has revealed rare reports of alteration of warfarin effect, including elevation of prothrombin times.
Intervention: | Frequently reevaluate the prothrombin time of patients on warfarin for signs of an interaction and adjust the dosage of warfarin as needed.

8 USE IN SPECIFIC POPULATIONS

8.1 Pregnancy

Risk Summary

Use of opioid analgesics for an extended period of time during pregnancy may cause neonatal opioid withdrawal syndrome [see Warnings and Precautions (5.4)] . Available data with tramadol hydrochloride and acetaminophen in pregnant women are insufficient to inform a drug-associated risk for major birth defects and miscarriage.

In animal reproduction studies, the combination of tramadol and acetaminophen decreased fetal weights and increased supernumerary ribs at 1.6 times the maximum recommended human daily dosage (MRHD). In separate animal reproduction studies, tramadol administration alone during organogenesis decreased fetal weights and reduced ossification in mice, rats, and rabbits at 1.4, 0.6, and 3.6 times the maximum recommended human daily dosage (MRHD). Tramadol decreased pup body weight and increased pup mortality at 1.2 and 1.9 times the MRHD.

Reproductive and developmental studies in rats and mice from the published literature identified adverse events at clinically relevant doses with acetaminophen. Treatment of pregnant rats with doses of acetaminophen approximately 1.3 times the maximum human daily dose (MRHD) showed evidence of fetotoxicity and increases in bone variations in the fetuses. In another study, necrosis was observed in the liver and kidney of both pregnant rats and fetuses at doses approximately 1.9 times the MHDD. In mice treated with acetaminophen at doses within the clinical dosing range, cumulative adverse effects on reproduction were seen in a continuous breeding study. A reduction in number of litters of the parental mating pair was observed as well as retarded growth and abnormal sperm in their offspring and reduced birth weight in the next generation [see Data]. Based on animal data, advise pregnant women of the potential risk to a fetus.

All pregnancies have a background risk of birth defect, loss, or other adverse outcomes. In the U.S. general population, the estimated background risk of major birth defects and miscarriage in clinically recognized pregnancies is 2 to 4% and 15 to 20%, respectively.

Clinical Considerations

Fetal/Neonatal Adverse Reactions

Use of opioid analgesics for an extended period of time during pregnancy for medical or nonmedical purposes can result in respiratory depression and physical dependence in the neonate and neonatal opioid withdrawal syndrome shortly after birth.

Neonatal opioid withdrawal syndrome presents as irritability, hyperactivity and abnormal sleep pattern, high pitched cry, tremor, vomiting, diarrhea and failure to gain weight. The onset, duration, and severity of neonatal opioid withdrawal syndrome vary based on the specific opioid used, duration of use, timing and amount of last maternal use, and rate of elimination of the drug by the newborn. Observe newborns for symptoms and signs of neonatal opioid withdrawal syndrome and manage accordingly [see Warnings and Precautions (5.4)] .

Neonatal seizures, neonatal withdrawal syndrome, fetal death and stillbirth have been reported with tramadol hydrochloride during postmarketing.

Labor or Delivery

Tramadol hydrochloride and acetaminophen is not recommended for use in pregnant women during or immediately prior to labor, when other analgesic techniques are more appropriate. Opioids cross the placenta and may produce respiratory depression and psycho-physiologic effects in neonates. An opioid overdose reversal agent, such as naloxone or nalmefene, must be available for reversal of opioid-induced respiratory depression in the neonate. Tramadol hydrochloride and acetaminophen is not recommended for use in pregnant women during or immediately prior to labor, when other analgesic techniques are more appropriate. Opioid analgesics, including tramadol hydrochloride and acetaminophen, can prolong labor through actions which temporarily reduce the strength, duration, and frequency of uterine contractions. However, this effect is not consistent and may be offset by an increased rate of cervical dilation, which tends to shorten labor. Monitor neonates exposed to opioid analgesics during labor for signs of excess sedation and respiratory depression.

Tramadol has been shown to cross the placenta. The mean ratio of serum tramadol in the umbilical veins compared to maternal veins was 0.83 for 40 women given tramadol during labor.

The effect of tramadol hydrochloride and acetaminophen, if any, on the later growth, development, and functional maturation of the child is unknown.

Data

Animal Data

No drug-related teratogenic effects were observed in the progeny of rats treated orally with tramadol and acetaminophen. The tramadol/acetaminophen combination product was shown to be embryotoxic and fetotoxic in rats at a maternally toxic dose, 50/434 mg/kg tramadol/acetaminophen (1.6 times the maximum daily human tramadol/acetaminophen dosage), but was not teratogenic at this dose level. Embryo and fetal toxicity consisted of decreased fetal weights and increased supernumerary ribs. Tramadol has been shown to be embryotoxic and fetotoxic in mice, (120 mg/kg), rats (25 mg/kg) and rabbits (75 mg/kg) at maternally toxic dosages, but was not teratogenic at these dose levels. These doses on a mg/m^2basis are 1.9, 0.8, and 4.9 times the maximum recommended human daily dosage (MRHD) for mouse, rat and rabbit, respectively.

No drug-related teratogenic effects were observed in progeny of mice (up to 140 mg/kg), rats (up to 80 mg/kg) or rabbits (up to 300 mg/kg) treated with tramadol by various routes. Embryo and fetal toxicity consisted primarily of decreased fetal weights, skeletal ossification and increased supernumerary ribs at maternally toxic dose levels. Transient delays in developmental or behavioral parameters were also seen in pups from rat dams allowed to deliver. Embryo and fetal lethality were reported only in one rabbit study at 300 mg/kg, a dose that would cause extreme maternal toxicity in the rabbit. The dosages listed for mouse, rat and rabbit are 2.3, 2.6, and 19 times the MRHD, respectively.

Tramadol alone was evaluated in peri- and post-natal studies in rats. Progeny of dams receiving oral (gavage) dose levels of 50 mg/kg (300 mg/m^2or 1.6 times the maximum daily human tramadol dosage) or greater had decreased weights, and pup survival was decreased early in lactation at 80 mg/kg (480 mg/m^2or 2.6 times the maximum daily human tramadol dosage).

Studies in pregnant rats that received oral acetaminophen during organogenesis at doses up to 1.3 times the maximum human daily dose (MHDD = 2.6 grams/day, based on a body surface area comparison) showed evidence of fetotoxicity (reduced fetal weight and length) and a dose- related increase in bone variations (reduced ossification and rudimentary rib changes). Offspring had no evidence of external, visceral, or skeletal malformations.

When pregnant rats received oral acetaminophen throughout gestation at doses of 1.9-times the MHDD (based on a body surface area comparison), areas of necrosis occurred in both the liver and kidney of pregnant rats and fetuses. These effects did not occur in animals that received oral acetaminophen at doses 0.5-times the MHDD, based on a body surface area comparison.

In a continuous breeding study, pregnant mice received 0.25, 0.5, or 1% acetaminophen via the diet (357, 715, or 1430 mg/kg/day). These doses are approximately 0.7, 1.3, and 2.7 times the MHDD, respectively, based on a body surface area comparison. A dose-related reduction in body weights of fourth and fifth litter offspring of the treated mating pair occurred during lactation and post-weaning at all doses. Animals in the high dose group had a reduced number of litters per mating pair, male offspring with an increased percentage of abnormal sperm, and reduced birth weights in the next generation pups.

8.2 Lactation

Risk Summary

Tramadol hydrochloride and acetaminophen is not recommended for obstetrical preoperative medication or for post-delivery analgesia in nursing mothers because its safety in infants and newborns has not been studied.

Tramadol and its metabolite, O-desmethyl tramadol (M1), are present in human milk. There is no information on the effects of the drug on the breastfed infant or the effects of the drug on milk production. The M1 metabolite is more potent than tramadol in mu opioid receptor binding [see Clinical Pharmacology (12.1)]. Published studies have reported tramadol and M1 in colostrum with administration of tramadol to nursing mothers in the early post-partum period. Women who are ultra-rapid metabolizers of tramadol may have higher than expected serum levels of M1, potentially leading to higher levels of M1 in breast milk that can be dangerous in their breastfed infants. In women with normal tramadol metabolism, the amount of tramadol secreted into human milk is low and dose-dependent. Because of the potential for serious adverse reactions, including excess sedation and respiratory depression in a breastfed infant, advise patients that breastfeeding is not recommended during treatment with tramadol hydrochloride and acetaminophen.

Clinical Considerations

If infants are exposed to tramadol hydrochloride and acetaminophen through breast milk, they should be monitored for excess sedation and respiratory depression. Withdrawal symptoms can occur in breastfed infants when maternal administration of an opioid analgesic is stopped, or when breast-feeding is stopped.

Data

Following a single IV 100 mg dose of tramadol, the cumulative excretion in breast milk within 16 hours post dose was 100 mcg of tramadol (0.1% of the maternal dose) and 27 mcg of M1.

8.3 Females and Males of Reproductive Potential

Infertility

Use of opioids for an extended period of time may cause reduced fertility in females and males of reproductive potential. It is not known whether these effects on fertility are reversible [see Adverse Reactions (6.2), Clinical Pharmacology (12.2), Nonclinical Toxicology (13.1)] .

8.4 Pediatric Use

The safety and effectiveness of tramadol hydrochloride and acetaminophen in pediatric patients have not been established.

Life-threatening respiratory depression and death have occurred in children who received tramadol [see Warnings and Precautions (5.6)] . In some of the reported cases, these events followed tonsillectomy and/or adenoidectomy, and one of the children had evidence of being an ultra-rapid metabolizer of tramadol (i.e., multiple copies of the gene for cytochrome P450 isoenzyme 2D6). Children with sleep apnea may be particularly sensitive to the respiratory depressant effects of tramadol.

Because of the risk of life-threatening respiratory depression and death:

- Tramadol hydrochloride and acetaminophen is contraindicated for all children younger than age 12 years of age [see Contraindications (4)] .
- Tramadol hydrochloride and acetaminophen is contraindicated for postoperative management in pediatric patients younger than 18 years of age following tonsillectomy and/or adenoidectomy [see Contraindications (4)] .

- Avoid the use of tramadol hydrochloride and acetaminophen in adolescents 12 to 18 years of age who have other risk factors that may increase their sensitivity to the respiratory depressant effects of tramadol unless the benefits outweigh the risks. Risk factors include conditions associated with hypoventilation such as postoperative status, obstructive sleep apnea, obesity, severe pulmonary disease, neuromuscular disease, and concomitant use of other medications that cause respiratory depression.

8.5 Geriatric Use

Elderly patients (65 years of age or older) may have increased sensitivity to tramadol. In general, use caution when selecting a dosage for an elderly patient, usually starting at the low end of the dosing range, reflecting the greater frequency of decreased hepatic, renal, or cardiac function and of concomitant disease or other drug therapy.

Respiratory depression is the chief risk for elderly patients treated with opioids, and has occurred after large initial doses were administered to patients who were not opioid-tolerant or when opioids were co-administered with other agents that depress respiration. Titrate the dosage of tramadol hydrochloride and acetaminophen slowly in geriatric patients and frequently reevaluate the patient for signs of central nervous system and respiratory depression [see Warnings and Precautions (5.2)].

Tramadol and acetaminophen are known to be substantially excreted by the kidney, and the risk of adverse reactions to this drug may be greater in patients with impaired renal function. Because elderly patients are more likely to have decreased renal function, care should be taken in dose selection, and it may be useful to regularly evaluate renal function.

8.6 Hepatic Impairment

The pharmacokinetics and tolerability of tramadol hydrochloride and acetaminophen in patients with impaired hepatic function have not been studied. Based on information using tramadol immediate-release tablets in subjects with advanced cirrhosis of the liver, tramadol exposure was higher and half-lives of tramadol and active metabolite M1 were longer than in subjects with normal hepatic function [see Clinical Pharmacology (12.3)].

As tramadol and acetaminophen are both extensively metabolized by the liver, the use of tramadol hydrochloride and acetaminophen in patients with hepatic impairment is not recommended [see Warnings and Precautions (5.9)] .

8.7 Renal Impairment

The pharmacokinetics and tolerability of tramadol hydrochloride and acetaminophen in patients with renal impairment has not been studied. Based on studies using tramadol extended-release tablets, the excretion of tramadol and metabolite M1 is reduced in patients with creatinine clearance of less than 30 mL/min. In patients with creatinine clearances of less than 30 mL/min, it is recommended that the dosage of tramadol hydrochloride and acetaminophen not exceed 2 tablets every 12 hours. [see Dosage and Administration (2.3)] . The total amount of tramadol and M1 removed during a 4 hour dialysis period is less than 7% of the administered dose based on studies using tramadol alone. Regularly evaluate closely for signs of respiratory depression, sedation, and hypotension.

8.8 Sex

Tramadol clearance was 20% higher in female subjects compared to males in four Phase 1 studies of tramadol hydrochloride and acetaminophen in 50 male and 34 female healthy subjects. The clinical significance of this difference is unknown.

9 DRUG ABUSE AND DEPENDENCE

9.1 Controlled Substance

Tramadol hydrochloride and acetaminophen tablets contains tramadol, a Schedule IV controlled substance.

9.2 Abuse

Tramadol hydrochloride and acetaminophen tablets contains tramadol, a substance with potential for misuse and abuse, which can lead to the development of substance use disorder, including addiction [see Warnings and Precautions (5.1)] .

Misuse is the intentional use, for therapeutic purposes, of a drug by an individual in a way other than prescribed by a healthcare provider or for whom it was not prescribed.

Abuse is the intentional, non-therapeutic use of a drug, even once, for its desirable psychological or physiological effects.

Drug addiction is a cluster of behavioral, cognitive, and physiological phenomena that may include a strong desire to take the drug, difficulties in controlling drug use (e.g., continuing drug use despite harmful consequences, giving a higher priority to drug use than other activities and obligations), and possible tolerance or physical dependence.

Misuse and abuse of tramadol hydrochloride and acetaminophen tablets increases risk of overdose, which may lead to central nervous system and respiratory depression, hypotension, seizures, and death. The risk is increased with concurrent abuse of tramadol hydrochloride and acetaminophen tablets with alcohol and other CNS depressants. Abuse of and addiction to opioids in some individuals may not be accompanied by concurrent tolerance and symptoms of physical dependence. In addition, abuse of opioids can occur in the absence of addiction.

All patients treated with opioids require careful and frequent reevaluation for signs of misuse, abuse, and addiction, because use of opioid analgesic products carries the risk of addiction even under appropriate medical use. Patients at high risk of tramadol hydrochloride and acetaminophen tablets abuse include those with a history of prolonged use of any opioid including products containing tramadol, those with a history of drug or alcohol abuse, or those who use tramadol hydrochloride and acetaminophen tablets in combination with other abused drugs.

“Drug seeking” behavior is very common in persons with substance use disorders. Drug seeking tactics include emergency calls or visits near the end of office hours, refusal to undergo appropriate examination, testing or referral, repeated “loss” of prescriptions, tampering with prescriptions, and reluctance to provide prior medical records or contact information for other treating healthcare provider(s). “Doctor shopping” (visiting multiple prescribers to obtain additional prescriptions) is common among people who abuse drugs and people with substance use disorder. Preoccupation with achieving adequate pain relief can be appropriate behavior in a patient with inadequate pain control.

Tramadol hydrochloride and acetaminophen, like other opioids, can be diverted for nonmedical use into illicit channels of distribution. Careful record-keeping of prescribing information, including quantity, frequency, and renewal requests, as required by state and federal law, is strongly advised.

Proper assessment of the patient, proper prescribing practices, periodic reevaluation of therapy, and proper dispensing and storage are appropriate measures that help to limit abuse of opioid drugs.

Risks Specific to Abuse of Tramadol Hydrochloride and Acetaminophen Tablets

Abuse of tramadol hydrochloride and acetaminophen tablets poses a risk of overdose and death. The risk is increased with concurrent use of tramadol hydrochloride and acetaminophen tablets with alcohol and/or other CNS depressants.

Tramadol hydrochloride and acetaminophen tablets is approved for oral use only.

Parenteral drug abuse is commonly associated with transmission of infectious diseases such as hepatitis and HIV.

9.3 Dependence

Both tolerance and physical dependence can develop during use of opioid therapy.

Tolerance is a physiological state characterized by a reduced response to a drug after repeated administration (i.e., a higher dose of a drug is required to produce the same effect that was once obtained at a lower dose).

Physical dependence is a state that develops as a result of a physiological adaptation in response to repeated drug use, manifested by withdrawal signs and symptoms after abrupt discontinuation or a significant dosage reduction of a drug.

Withdrawal may be precipitated through the administration of drugs with opioid antagonist activity (e.g., naloxone, nalmefene), mixed agonist/antagonist analgesics (e.g., pentazocine, butorphanol, nalbuphine), or partial agonists (e.g., buprenorphine). Physical dependence may not occur to a clinically significant degree until after several days to weeks of continued use.

Do not rapidly reduce or abruptly discontinue tramadol hydrochloride and acetaminophen tablets in a patient physically dependent on opioids. Rapid tapering of tramadol hydrochloride and acetaminophen tablets in a patient physically dependent on opioids may lead to serious withdrawal symptoms, uncontrolled pain and suicide. Rapid discontinuation has also been associated with attempts to find other sources of opioid analgesics, which may be confused with drug-seeking for abuse.

When discontinuing tramadol hydrochloride and acetaminophen tablets, gradually taper the dosage using a patient-specific plan that considers the following: the dose of the tramadol hydrochloride and acetaminophen tablets the patient has been taking, the duration of treatment, and the physical and psychological attributes of the patient. To improve the likelihood of a successful taper and minimize withdrawal symptoms, it is important that the opioid tapering schedule is agreed upon by the patient. In patients taking opioids for an extended period of time at high doses, ensure that a multimodal approach to pain management, including mental health support (if needed), is in place prior to initiating an opioid analgesic taper [see Dosage and Administration (2.5), Warnings and Precautions (5.21)].

Infants born to mothers physically dependent on opioids will also be physically dependent and may exhibit respiratory difficulties and withdrawal signs [see Use in Specific Populations (8.1)] .

10 OVERDOSAGE

Clinical Presentation

Tramadol hydrochloride and acetaminophen tablet is a combination drug. The clinical presentation of overdose may include the signs and symptoms of tramadol toxicity, acetaminophen toxicity or both. The initial symptoms of tramadol overdosage may include respiratory depression and/or seizures. The initial symptoms seen within the first 24 hours following an acetaminophen overdose are: anorexia, nausea, vomiting, malaise, pallor and diaphoresis.

Tramadol

Acute overdosage with tramadol can be manifested by respiratory depression, somnolence progressing to stupor or coma, skeletal muscle flaccidity, cold and clammy skin, constricted pupils, and, in some cases, pulmonary edema, bradycardia, QT prolongation, hypotension, partial or complete airway obstruction, atypical snoring, seizures, and death. Marked mydriasis rather than miosis may be seen with hypoxia in overdose situations [see Clinical Pharmacology (12.2)] . Toxic leukoencephalopathy has been reported after opioid overdose and can present hours, days, or weeks after apparent recovery from the initial intoxication.

Deaths due to overdose have been reported with abuse and misuse of tramadol [see Warnings and Precautions (5.1)]. Review of case reports has indicated that the risk of fatal overdose is further increased when tramadol is abused concurrently with alcohol or other CNS depressants, including other opioids.

Acetaminophen

In acute acetaminophen overdosage, dose-dependent, potentially fatal hepatic necrosis is the most serious adverse effect. Renal tubular necrosis, hypoglycemic coma, and thrombocytopenia also occur. Plasma acetaminophen levels > 300 mcg/mL at 4 hours after oral ingestion were associated with hepatic damage in 90% of patients; minimal hepatic damage is anticipated if plasma levels at 4 hours are < 150 mcg/mL or < 37.5 mcg/mL at 12 hours after ingestion. Early symptoms following a potentially hepatotoxic overdose may include: nausea, vomiting, diaphoresis, and general malaise. Clinical and laboratory evidence of hepatic toxicity may not be apparent until 48 to 72 hours post-ingestion.

Treatment of Overdose

A single or multiple drug overdose with tramadol and acetaminophen is a potentially lethal polydrug overdose. Immediate treatment includes support of cardiorespiratory function and measures to reduce drug absorption. Oxygen, intravenous fluids, vasopressors, assisted ventilation, and other supportive measures should be employed as indicated. Because strategies for the management of overdose are continually evolving, it is advisable to contact a poison control center (where available) to determine the latest recommendations for the management of an overdose.

Tramadol

In case of overdose, priorities are the re-establishment of a patent and protected airway and institution of assisted or controlled ventilation, if needed. Employ other supportive measures (including oxygen and vasopressors) in the management of circulatory shock and pulmonary edema as indicated. Cardiac arrest or arrhythmias will require advanced life-support measures.

For clinically significant respiratory or circulatory depression secondary to opioid overdose, administer an opioid overdose reversal agent such as naloxone or nalmefene.

While an opioid overdose reversal agent will reverse some, but not all, symptoms caused by overdosage with tramadol, the risk of seizures is also increased with reversal agent administration. In animals, convulsions following the administration of toxic doses of tramadol hydrochloride and acetaminophen could be suppressed with barbiturates or benzodiazepines but were increased with naloxone. Naloxone administration did not change the lethality of an overdose in mice. Hemodialysis is not expected to be helpful in an overdose because it removes less than 7% of the administered dose in a 4-hour dialysis period.

Because the duration of opioid reversal is expected to be less than the duration of action of tramadol in tramadol hydrochloride and acetaminophen tablets, carefully monitor the patient until spontaneous respiration is reliably re-established. If the response to an opioid overdose reversal agent is suboptimal or only brief in nature, administer additional reversal agent as directed by the product’s prescribing information.

In an individual physically dependent on opioids, administration of the recommended usual dosage of the opioid overdose reversal agent will precipitate an acute withdrawal syndrome. The severity of the withdrawal symptoms experienced will depend on the degree of physical dependence and the dose of the reversal agent administered. If a decision is made to treat serious respiratory depression in the physically dependent patient, administration of the reversal agent should be begun with care and by titration with smaller than usual doses of the reversal agent.

Acetaminophen

If an acetaminophen overdose is suspected, obtain a serum acetaminophen assay as soon as possible, but no sooner than 4 hours following oral ingestion. Obtain liver function studies initially and repeat at 24-hour intervals. Administer the antidote N-acetylcysteine (NAC) as early as possible. As a guide to treatment of acute ingestion, the acetaminophen level can be plotted against time since oral ingestion on a nomogram Rumack-Matthew). The lower toxic line on the nomogram is equivalent to 150 mcg/mL at 4 hours and 37.5 mcg/mL at 12 hours. If serum level is above the lower line, administer the entire course of NAC treatment. Withhold NAC therapy if the acetaminophen level is below the lower line.

Serum acetaminophen levels should be obtained immediately if the patient presents 4 hours or more after ingestion to assess potential risk of hepatotoxicity; acetaminophen levels drawn less than 4 hours post-ingestion may be misleading. To obtain the best possible outcome, NAC should be administered as soon as possible where impending or evolving liver injury is suspected. Intravenous NAC may be administered when circumstances preclude oral administration.

Vigorous supportive therapy is required in severe intoxication. Procedures to limit the continuing absorption of the drug must be readily performed since the hepatic injury is dose-dependent and occurs early in the course of intoxication.

11 DESCRIPTION

Tramadol hydrochloride and acetaminophen tablet USP combines two analgesics, tramadol hydrochloride and opioid agonist, and acetaminophen.

The chemical name for tramadol hydrochloride is (±)cis-2-[(dimethylamino)methyl]-1-(3-methoxyphenyl) cyclohexanol hydrochloride. Its structural formula is:

The molecular weight of tramadol hydrochloride is 299.84. Tramadol hydrochloride USP is a white, bitter, crystalline, and odorless powder.

The chemical name for acetaminophen is N-acetyl-p-aminophenol. Its structural formula is:

The molecular weight of acetaminophen is 151.17. Acetaminophen USP is an analgesic and antipyretic agent which occurs as a white, odorless, crystalline powder, possessing a slightly bitter taste.

Tramadol hydrochloride and acetaminophen tablets, USP contain 37.5 mg of tramadol hydrochloride, USP and 325 mg acetaminophen, USP and are light yellow in color. Inactive ingredients in the tablets are powdered cellulose, pregelatinized starch, sodium starch glycolate, corn starch, magnesium stearate and OPADRY®Light Yellow.

OPADRY®Light Yellow consists of the following ingredients:

Hypromellose 2910

Titanium Dioxide

Polyethylene Glycol 400

Iron oxide yellow

Polysorbate 80

Meets USP Dissolution Test 2.

12 CLINICAL PHARMACOLOGY

The following information is based on studies of tramadol alone or acetaminophen alone, except where otherwise noted:

12.1 Mechanism of Action

Tramadol hydrochloride and acetaminophen tablet contains tramadol, an opioid agonist and inhibitor of norepinephrine and serotonin re-uptake, and acetaminophen. Although the mode of action of tramadol is not completely understood, the analgesic effect of tramadol is believed to be due to both binding to µ-opioid receptors and weak inhibition of reuptake of norepinephrine and serotonin.

Opioid activity of tramadol is due to both low affinity binding of the parent compound and higher affinity binding of the O-demethylated metabolite M1 to µ-opioid receptors. In animal models, M1 is up to 6 times more potent than tramadol in producing analgesia and 200 times more potent in µ-opioid binding. Tramadol-induced analgesia is only partially antagonized by the opiate antagonist naloxone in several animal tests. The relative contribution of both tramadol and M1 to human analgesia is dependent upon the plasma concentrations of each compound [see Clinical Pharmacology (12.3)] .

Tramadol has been shown to inhibit reuptake of norepinephrine and serotonin in vitro, as have some other opioid analgesics. These mechanisms may contribute independently to the overall analgesic profile of tramadol.

Acetaminophen is a non-opioid, non-salicylate analgesic. The site and mechanism for the analgesic effect of acetaminophen has not been determined but is thought to primarily involve central actions.

12.2 Pharmacodynamics

Effects on the Central Nervous System

Tramadol produces respiratory depression by direct action on brain stem respiratory centers. The respiratory depression involves a reduction in the responsiveness of the brain stem respiratory centers to both increases in carbon dioxide tension and electrical stimulation.

Tramadol causes miosis, even in total darkness. Pinpoint pupils are a sign of opioid overdose but are not pathognomonic (e.g., pontine lesions of hemorrhagic or ischemic origins may produce similar findings). Marked mydriasis rather than miosis may be seen due to hypoxia in overdose situations.

Effects on the Gastrointestinal Tract and Other Smooth Muscle

Tramadol causes a reduction in motility associated with an increase in smooth muscle tone in the antrum of the stomach and duodenum. Digestion of food in the small intestine is delayed and propulsive contractions are decreased. Propulsive peristaltic waves in the colon are decreased, while tone may be increased to the point of spasm resulting in constipation. Other opioid-induced effects may include a reduction in biliary and pancreatic secretions, spasm of sphincter of Oddi, transient elevations in serum amylase, and opioid-induced esophageal dysfunction (OIED).

Effects on the Cardiovascular System

Tramadol produces peripheral vasodilation which may result in orthostatic hypotension or syncope. Manifestations of histamine release and/or peripheral vasodilation may include pruritus, flushing, red eyes, sweating, and/or orthostatic hypotension.

The effect of oral tramadol on the QTcF interval was evaluated in a double-blind, randomized, four-way crossover, placebo- and positive- (moxifloxacin) controlled study in 68 adult male and female healthy subjects. At a 600 mg/day dose (1.5-fold the maximum immediate-release daily dose), the study demonstrated no significant effect on the QTcF interval.

Effects on the Endocrine System

Opioids inhibit the secretion of adrenocorticotropic hormone (ACTH), cortisol, and luteinizing hormone (LH) in humans [see Warnings and Precautions (5.12), Adverse Reactions (6.2)] . They also stimulate prolactin, growth hormone (GH) secretion, and pancreatic secretion of insulin and glucagon.

Use of opioids for an extended period of time may influence the hypothalamic-pituitary-gonadal axis, leading to androgen deficiency that may manifest as low libido, impotence, erectile dysfunction, amenorrhea, or infertility. The causal role of opioids in the clinical syndrome of hypogonadism is unknown because the various medical, physical, lifestyle, and psychological stressors that may influence gonadal hormone levels have not been adequately controlled for in studies conducted to date [see Adverse Reactions (6.2)] .

Effects on the Immune System

Opioids have been shown to have a variety of effects on components of the immune system in in vitroand animal models. The clinical significance of these findings is unknown. Overall, the effects of opioids appear to be modestly immunosuppressive.

Concentration-Efficacy Relationships

The minimum effective analgesic concentration will vary widely among patients, especially among patients who have been previously treated with opioid agonists. The minimum effective analgesic concentration of tramadol for any individual patient may increase over time due to an increase in pain, the development of a new pain syndrome and/or the development of analgesic tolerance [see Dosage and Administration (2.1)] .

Concentration-Adverse Reaction Relationships

There is a relationship between increasing tramadol plasma concentration and increasing frequency of dose-related opioid adverse reactions such as nausea, vomiting, CNS effects, and respiratory depression. In opioid-tolerant patients, the situation may be altered by the development of tolerance to opioid-related adverse reactions [see Dosage and Administration (2.1, 2.3)] .

12.3 Pharmacokinetics

Tramadol is administered as a racemate and both the [-] and [+] forms of both tramadol and M1 are detected in the circulation.

Absorption

The absolute bioavailability of tramadol from tramadol hydrochloride and acetaminophen tablets has not been determined. Tramadol has a mean absolute bioavailability of approximately 75% following administration of a single 100 mg oral dose of tramadol hydrochloride tablets. The mean peak plasma concentration of racemic tramadol and M1 after administration of two tramadol hydrochloride and acetaminophen tablets occurs at approximately two and three hours, respectively, post-dose.

The pharmacokinetics of plasma tramadol and acetaminophen following oral administration of one tramadol hydrochloride and acetaminophen tablet are shown in Table 3. Tramadol has a slower absorption and longer half-life when compared to acetaminophen.

Table 3: Summary of Mean (±SD) Pharmacokinetic Parameters of the (+)- and (-) Enantiomers of Tramadol and M1 and Acetaminophen Following A Single Oral Dose Of One Tramadol/Acetaminophen Combination Tablet (37.5 mg/325 mg) in Volunteers

Parametera | (+)-Tramadol |  | (-)-Tramadol |  | (+)-M1 |  | (-)-M1 |  | acetaminophen
Cmax(ng/mL) | 64.3 | (9.3) | 55.5 | (8.1) | 10.9 | (5.7) | 12.8 | (4.2) | 4.2 | (0.8)
tmax(h) | 1.8 | (0.6) | 1.8 | (0.7) | 2.1 | (0.7) | 2.2 | (0.7) | 0.9 | (0.7)
CL/F (mL/min) | 588 | (226) | 736 | (244) | - | - | - | - | 365 | (84)
t1/2(h) | 5.1 | (1.4) | 4.7 | (1.2) | 7.8 | (3) | 6.2 | (1.6) | 2.5 | (0.6)

aFor acetaminophen, Cmaxwas measured as mcg/mL.

A single-dose pharmacokinetic study of tramadol hydrochloride and acetaminophen in volunteers showed no drug interactions between tramadol and acetaminophen.

Upon multiple oral dosing to steady state, however, the bioavailability of tramadol and metabolite M1 was lower for the combination tablets compared to tramadol administered alone. The decrease in AUC was 14% for (+)-tramadol, 10.4% for (-)-tramadol, 11.9% for (+)-M1, and 24.2% for (-)-M1. The cause of this reduced bioavailability is not clear.

Peak plasma concentrations of acetaminophen occur within one hour and are not affected by co-administration with tramadol. Following single- or multiple-dose administration of tramadol hydrochloride and acetaminophen, no significant change in acetaminophen pharmacokinetics was observed when compared to acetaminophen given alone.

Food Effect

When tramadol hydrochloride and acetaminophen tablet was administered with food, the time to peak plasma concentration was delayed for approximately 35 minutes for tramadol and almost one hour for acetaminophen. However, peak plasma concentrations, and the extents of absorption, of tramadol and acetaminophen were not affected. The clinical significance of this difference is unknown.

Distribution

The volume of distribution of tramadol was 2.6 and 2.9 L/kg in male and female subjects, respectively, following a 100 mg intravenous dose. The binding of tramadol to human plasma proteins is approximately 20% and binding also appears to be independent of concentration up to 10 mcg/mL. Saturation of plasma protein binding occurs only at concentrations outside the clinically relevant range.

Acetaminophen appears to be widely distributed throughout most body tissues except fat. Its apparent volume of distribution is about 0.9 L/kg. A relative small portion (~20%) of acetaminophen is bound to plasma protein.

Elimination

Tramadol is eliminated primarily through metabolism by the liver and the metabolites are eliminated primarily by the kidneys. The mean (SD) apparent total clearance of tramadol after a single 37.5 mg dose is 588 (226) mL/min for the (+) isomer and 736 (244) mL/min for the (-) isomer. The plasma elimination half-lives of racemic tramadol and M1 are approximately 5 to 6 and 7 hours, respectively, after administration of tramadol hydrochloride and acetaminophen tablets. The apparent plasma elimination half-life of racemic tramadol increased to 7 to 9 hours upon multiple dosing of tramadol hydrochloride and acetaminophen tablets.

The half-life of acetaminophen is about 2 to 3 hours in adults. It is somewhat shorter in children and somewhat longer in neonates and in cirrhotic patients. Acetaminophen is eliminated from the body primarily by formation of glucuronide and sulfate conjugates in a dose dependent manner.

Metabolism

Following oral administration, tramadol is extensively metabolized by a number of pathways, including CYP2D6 and CYP3A4, as well as by conjugation of parent and metabolites. The major metabolic pathways appear to be N- and O-demethylation and glucuronidation or sulfation in the liver. Metabolite M1 (O-desmethyltramadol) is pharmacologically active in animal models. Formation of M1 is dependent on CYP2D6 and as such is subject to inhibition, which may affect the therapeutic response [see Drug Interactions (7)] .

Approximately 7% of the population has reduced activity of the CYP2D6 isoenzyme of cytochrome P450. These individuals are “poor metabolizers” of debrisoquine, dextromethorphan, and tricyclic antidepressants, among other drugs. Based on a population PK analysis of Phase 1 studies in healthy subjects, concentrations of tramadol were approximately 20% higher in “poor metabolizers” versus “extensive metabolizers,” while M1 concentrations were 40% lower. In vitrodrug interaction studies in human liver microsomes indicate that inhibitors of CYP2D6 such as fluoxetine and its metabolite norfluoxetine, amitriptyline, and quinidine inhibit the metabolism of tramadol to various degrees. The full pharmacological impact of these alterations in terms of either efficacy or safety is unknown.

Acetaminophen is primarily metabolized in the liver by first-order kinetics and involves three principal separate pathways:

a) conjugation with glucuronide;

b) conjugation with sulfate; and

c) oxidation via the cytochrome, P450-dependent, mixed-function oxidase enzyme pathway to form a reactive intermediate metabolite, which conjugates with glutathione and is then further metabolized to form cysteine and mercapturic acid conjugates. The principal cytochrome P450 isoenzyme involved appears to be CYP2E1, with CYP1A2 and CYP3A4 as additional pathways.

In adults, the majority of acetaminophen is conjugated with glucuronic acid and, to a lesser extent, with sulfate. These glucuronide-, sulfate-, and glutathione-derived metabolites lack biologic activity. In premature infants, newborns, and young infants, the sulfate conjugate predominates.

Excretion

Approximately 30% of the tramadol dose is excreted in the urine as unchanged drug, whereas 60% of the dose is excreted as metabolites.

Less than 9% of acetaminophen is excreted unchanged in the urine.

Special Populations

Hepatic Impairment

Pharmacokinetics of tramadol was studied in patients with mild or moderate hepatic impairment after receiving multiple doses of tramadol extended-release 100 mg. The exposure of (+)-and (-) -tramadol was similar in mild and moderate hepatic impairment patients in comparison to patients with normal hepatic function. However, exposure of (+) - and (-)-M1 decreased ~50% with increased severity of the hepatic impairment (from normal to mild and moderate). The pharmacokinetics of tramadol after the administration of tramadol extended-release has not been studied in patients with severe hepatic impairment. After the administration of tramadol immediate-release tablets to patients with advanced cirrhosis of the liver, tramadol area under the plasma concentration time curve was larger and the tramadol and M1 half-lives were longer than subjects with normal hepatic function [see Use in Specific Populations (8.6)].

Renal Impairment

Impaired renal function results in a decreased rate and extent of excretion of tramadol and its active metabolite, M1. The pharmacokinetics of tramadol were studied in patients with mild or moderate renal impairment after receiving multiple doses of tramadol extended-release 100 mg. There is no consistent trend observed for tramadol exposure related to renal function in patients with mild (CLcr: 50 to 80 mL/min) or moderate (CLcr: 30 to 50 mL/min) renal impairment in comparison to patients with normal renal function. However, exposure of M1 increased 20 to 40% with increased severity of the renal impairment (from normal to mild and moderate). tramadol extended-release has not been studied in patients with severe renal impairment (CLcr < 30 mL/min). The total amount of tramadol and M1 removed during a 4-hour dialysis period is less than 7% of the administered dose [see Dosage and Administration (2.4), Use in Specific Populations (8.7)] .

Geriatric Population

A population pharmacokinetic analysis of data obtained from a clinical trial in patients with chronic pain treated with tramadol hydrochloride and acetaminophen, which included 55 patients between 65 and 75 years of age and 19 patients over 75 years of age, showed no significant changes in the pharmacokinetics of tramadol and acetaminophen in elderly patients with normal renal and hepatic function [see Use in Specific Populations (8.5)]

Sex

Tramadol clearance was 20% higher in female subjects compared to males on four Phase 1 studies of tramadol hydrochloride and acetaminophen in 50 male and 34 female healthy subjects.

Poor / Extensive Metabolizers, CYP2D6

The formation of the active metabolite, M1, is mediated by CYP2D6. Approximately 7% of the population has reduced activity of the CYP2D6 isoenzyme of cytochrome P-450. These individuals are “poor metabolizers” of debrisoquine, dextromethorphan, and tricyclic antidepressants, among other drugs. Based on a population PK analysis of Phase 1 studies with immediate-release tablets in healthy subjects, concentrations of tramadol were approximately 20% higher in “poor metabolizers” versus “extensive metabolizers,” while M1 concentrations were 40% lower.

Drug Interaction Studies

CYP2D6 Inhibitors

In vitrodrug interaction studies in human liver microsomes indicate that inhibitors of CYP2D6 (fluoxetine, norfluoxetine, amitriptyline, and quinidine) inhibit the metabolism of tramadol to various degrees, suggesting that concomitant administration of these compounds could result in increases in tramadol concentrations and decreased concentrations of M1. The full pharmacological impact of these alterations in terms of either efficacy or safety is unknown.

Quinidine

Tramadol is metabolized to M1 by CYP2D6. A study was conducted to examine the effect of quinidine, a selective inhibitor of CYP2D6, on the pharmacokinetics of tramadol by administering 200 mg quinidine two hours before the administration of 100 mg tramadol extended release tablet. The results demonstrated that the exposure of tramadol increased 50 to 60% and the exposure of M1 decreased 50 to 60%. In vitrodrug interaction studies in human liver microsomes indicate that tramadol has no effect on quinidine metabolism [see Warnings and Precautions (5.7) and Drug Interactions (7)] .

Cimetidine

Concomitant administration of tramadol and cimetidine does not result in clinically significant changes in tramadol pharmacokinetics. Therefore, no alteration of the tramadol hydrochloride and acetaminophen dosage regimen is recommended.

CYP3A4 Inhibitors and Inducers

Tramadol is metabolized by CYP3A4. Administration of CYP3A4 inhibitors, such as ketoconazole and erythromycin, or CYP3A4 inducers, such as rifampin and St. John’s Wort, with tramadol may affect the metabolism of tramadol leading to altered tramadol exposure [see Warnings and Precautions (5.2and 5.7) and Drug Interactions (7)] .

Carbamazepine

Carbamazepine, a CYP3A4 inducer, increases tramadol metabolism. Patients taking carbamazepine may have a significantly reduced analgesic effect of tramadol. Concomitant administration of tramadol and carbamazepine is not recommended.

Potential for Tramadol to Affect Other Drugs

In vitrostudies indicate that tramadol is unlikely to inhibit the CYP3A4-mediated metabolism of other drugs when tramadol is administered concomitantly at therapeutic doses. Tramadol does not appear to induce its own metabolism in humans, since observed maximal plasma concentrations after multiple oral doses are higher than expected based on single dose data.

13 NONCLINICAL TOXICOLOGY

13.1 Carcinogenesis, Mutagenesis, Impairment of Fertility

There are no animal or laboratory studies on the combination product (tramadol and acetaminophen) to evaluate carcinogenesis, mutagenesis, or impairment of fertility. Data on the individual components are described below.

Carcinogenesis

A slight but statistically significant increase in two common murine tumors, pulmonary and hepatic, was observed in an NMRI mouse carcinogenicity study, particularly in aged mice. Mice were dosed orally up to 30 mg/kg in the drinking water (0.5 times the maximum recommended daily human dosage or MRHD) for approximately two years, although the study was not done with the Maximum Tolerated Dose. This finding is not believed to suggest risk in humans. No evidence of carcinogenicity was noted in a rat 2-year carcinogenicity study testing oral doses of up to 30 mg/kg in the drinking water (1 times the MRHD).

Long-term studies in mice and rats have been completed by the National Toxicology Program to evaluate the carcinogenic potential of acetaminophen. In 2-year feeding studies, F344/N rats and B6C3F1 mice were fed a diet containing acetaminophen up to 6000 ppm. Female rats demonstrated equivocal evidence of carcinogenic activity based on increased incidences of mononuclear cell leukemia at 1.2 times the maximum human daily dose (MHDD) of 2.6 grams/day, based on a body surface area comparison. In contrast, there was no evidence of carcinogenic activity in male rats (1.1 times) or mice (1.9 to 2.2 times the MHDD, based on a body surface area comparison).

Mutagenesis

Tramadol was mutagenic in the presence of metabolic activation in the mouse lymphoma assay. Tramadol was not mutagenic in the in vitro bacterial reverse mutation assay using Salmonellaand E. coli(Ames), the mouse lymphoma assay in the absence of metabolic activation, the in vitrochromosomal aberration assay, or the in vivomicronucleus assay in bone marrow.

Acetaminophen was not mutagenic in the bacterial reverse mutation assay (Ames test). In contrast, acetaminophen tested positive for induction of sister chromatid exchanges and chromosomal aberrations in in vitroassays using Chinese hamster ovary cells. In the published literature, acetaminophen has been reported to be clastogenic when administered a dose of 1500 mg/kg/day to the rat model (3.6-times the MHDD, based on a body surface area comparison). In contrast, no clastogenicity was noted at a dose of 750 mg/kg/day (2.8-times the MHDD, based on a body surface area comparison), suggesting a threshold effect.

Impairment of Fertility

No effects on fertility were observed for tramadol at oral dose levels up to 50 mg/kg in male rats and 75 mg/kg in female rats. These dosages are 1.6 and 2.4 times the MRHD [see Use in Specific Populations (8.3)] .

In studies of acetaminophen conducted by the National Toxicology Program, fertility assessments have been completed in Swiss mice via a continuous breeding study. There were no effects on fertility parameters in mice consuming up to 1.7 times the MHDD of acetaminophen, based on a body surface area comparison. Although there was no effect on sperm motility or sperm density in the epididymis, there was a significant increase in the percentage of abnormal sperm in mice consuming 1.7 times the MHDD (based on a body surface area comparison) and there was a reduction in the number of mating pairs producing a fifth litter at this dose, suggesting the potential for cumulative toxicity with chronic administration of acetaminophen near the upper limit of daily dosing.

Published studies in rodents report that oral acetaminophen treatment of male animals at doses that are 1.2 times the MHDD and greater (based on a body surface area comparison) result in decreased testicular weights, reduced spermatogenesis, reduced fertility, and reduced implantation sites in females given the same doses. These effects appear to increase with the duration of treatment. The clinical significance of these findings is not known.

14 CLINICAL STUDIES

14.1 Single-Dose Studies for Treatment of Acute Pain

In single-dose studies in acute pain, two tablets of tramadol hydrochloride and acetaminophen administered to patients with pain following oral surgical procedures provided greater relief than placebo or either of the individual components given at the same dose. The onset of pain relief after tramadol hydrochloride and acetaminophen tablet was faster than tramadol alone. Onset of analgesia occurred in less than one hour. The duration of pain relief after tramadol hydrochloride and acetaminophen tablet was longer than acetaminophen alone. Analgesia was generally comparable to that of the comparator, ibuprofen.

16 HOW SUPPLIED/STORAGE AND HANDLING

Tramadol hydrochloride and acetaminophen tablets USP, 37.5 mg/325 mg, are light yellow, oblong-shaped, biconvex, film-coated tablets debossed with “I 03” on one side and plain on the other side. They are available as follows:

Bottles of 90 tablets NDC 42571-119-90

Bottles of 100 tablets NDC 42571-119-01

Bottles of 500 tablets NDC 42571-119-05

Unit Dose Blister Cartons of 80 (8 x 10) tablets NDC 42571-119-23

Dispense in a tight container. Store at 20° to 25°C (68° to 77°F); excursions permitted to 15° to 30°C (59° to 86°F) [see USP Controlled Room Temperature].

Store tramadol hydrochloride and acetaminophen tablets securely and dispose of properly [see Patient Counseling Information (17)].

17 PATIENT COUNSELING INFORMATION

Advise the patient to read the FDA-approved patient labeling (Medication Guide).

Storage and Disposal

Because of the risks associated with accidental ingestion, misuse, and abuse, advise patients to store tramadol hydrochloride and acetaminophen tablets securely, out of sight and reach of children, and in a location not accessible by others, including visitors to the home .Inform patients that leaving tramadol hydrochloride and acetaminophen tablets unsecured can pose a deadly risk to others in the home [see Warnings and Precautions (5.1,5.21), Drug Abuse and Dependence (9.1)].

Advise patients and caregivers that when medicines are no longer needed, they should be disposed of promptly. Inform patients that medicine take-back options are the preferred way to safely dispose of most types of unneeded medicines. If no take back programs or Drug Enforcement Administration (DEA)-registered collectors are available, instruct patients to dispose of tramadol hydrochloride and acetaminophen tablets by following these four steps:

- Mix tramadol hydrochloride and acetaminophen tablets (do not crush) with an unpalatable substance such as dirt, cat litter, or used coffee grounds;
- Place the mixture in a container such as a sealed plastic bag;

- Throw the container in the household trash;

- Delete all personal information on the prescription label of the empty bottle.

Inform patients that they can visit www.fda.gov/drugdisposal for additional information on disposal of unused medicines.

Addiction, Abuse, and Misuse

Inform patients that the use of tramadol hydrochloride and acetaminophen tablets, even when taken as recommended, can result in addiction, abuse, and misuse, which can lead to overdose and death [see Warnings and Precautions (5.1)]. Instruct patients not to share tramadol hydrochloride and acetaminophen tablets with others and to take steps to protect tramadol hydrochloride and acetaminophen tablets from theft or misuse.

Life-Threatening Respiratory Depression

Inform patients of the risk of life-threatening respiratory depression, including information that the risk is greatest when starting tramadol hydrochloride and acetaminophen or when the dosage is increased, and that it can occur even at recommended dosages.

Educate patients and caregivers on how to recognize respiratory depression and emphasize the importance of calling 911 or getting emergency medical help right away in the event of a known or suspected overdose [see Warnings and Precautions (5.2)].

Accidental Ingestion

Inform patients that accidental ingestion, especially by children, may result in respiratory depression or death [see Warnings and Precautions (5.2)].

Interactions with Benzodiazepines or Other CNS Depressants

Inform patients and caregivers that potentially fatal additive effects may occur if tramadol hydrochloride and acetaminophen is used with benzodiazepines or other CNS depressants, including alcohol (e.g., non-benzodiazepine, sedative/hypnotics, anxiolytics, tranquilizers, muscle relaxants, general anesthetics, antipsychotics, gabapentinoids [gabapentin or pregabalin] and other opioids), and not to use these concomitantly unless supervised by a healthcare provider [see Warnings and Precautions (5.3), Drug Interactions (7)].

Patient Access to an Opioid Overdose Reversal Agent for the Emergency Treatment of Opioid Overdose

Inform patients and caregivers about opioid overdose reversal agents (e.g.,naloxone, nalmefene). Discuss the importance of having access to an opioid overdose reversal agent, especially if the patient has risk factors for overdose (e.g., concomitant use of CNS depressants, a history of opioid use disorder, or prior opioid overdose) or if there are household members (including children) or other close contacts at risk for accidental ingestion or opioid overdose.

Discuss with the patient the options for obtaining an opioid overdose reversal agent (e.g., prescription, over-the-counter, or as part of a community-based program) [see Dosage and Administration (2.2), Warnings and Precautions (5.3)] .

Educate patients and caregivers on how to recognize the signs and symptoms of an overdose.

Explain to patients and caregivers that effects of opioid overdose reversal agents like naloxone and nalmefene are temporary, and that they must call 911 or get emergency medical help right away in all cases of known or suspected opioid overdose, even if an opioid overdose reversal agent is administered [see Overdosage (10)] .

Advise patients and caregivers:

- how to treat with the overdose reversal agent in the event of an opioid overdose.
- to tell family and friends about the opioid overdose reversal agent, and to keep it in a place where family and friends can access it in an emergency.
- to read the Patient Information (or other educational material) that will come with their opioid overdose reversal agent. Emphasize the importance of doing this before an opioid emergency happens, so the patient and caregiver will know what to do.

Ultra-Rapid Metabolism of Tramadol and Other Risk Factors for Life-threatening Respiratory Depression in Children

Advise caregivers that tramadol hydrochloride and acetaminophen tablets are contraindicated in children younger than 12 years of age and in children younger than 18 years of age following tonsillectomy and/or adenoidectomy. Advise caregivers of children 12 to 18 years of age receiving tramadol hydrochloride and acetaminophen to monitor for signs of respiratory depression [see Warnings and Precautions (5.6)].

Hyperalgesia and Allodynia

Inform patients and caregivers not to increase opioid dosage without first consulting a clinician. Advise patients to seek medical attention if they experience symptoms of hyperalgesia, including worsening pain, increased sensitivity to pain, or new pain [see Warnings and Precautions (5.8); Adverse Reactions (6.2)].

Serotonin Syndrome

Inform patients that tramadol could cause a rare but potentially life-threatening condition, particularly during concomitant use with serotonergic drugs. Warn patients of the symptoms and signs of serotonin syndrome and to seek medical attention right away if symptoms develop. Instruct patients to inform their healthcare provider if they are taking, or plan to take serotonergic medications [see Warnings and Precautions (5.10)].

MAOI Interaction

Inform patients not to take tramadol hydrochloride and acetaminophen tablets while using any drugs that inhibit monoamine oxidase. Patients should not start MAOIs while taking tramadol hydrochloride and acetaminophen tablets [see Drug Interactions (7)].

Seizures

Inform patients that tramadol hydrochloride and acetaminophen tablets may cause seizures with concomitant use of serotonergic agents (including SSRIs, SNRIs, and triptans) or drugs that significantly reduce the metabolic clearance of tramadol [see Warnings and Precautions (5.11)].

Important Administration Instructions

Instruct patients how to properly take tramadol hydrochloride and acetaminophen tablets [see Dosage and Administration (2)].

- Do not adjust the dose of tramadol hydrochloride and acetaminophen tablets without consulting with a physician or other healthcare provider.
- Do not take more than 4000 milligrams of acetaminophen tablet per day and to call their healthcare provider if they took more than the recommended dose.

Important Discontinuation Instructions

In order to avoid developing withdrawal symptoms, instruct patients not to discontinue tramadol hydrochloride and acetaminophen tablets without first discussing a tapering plan with the prescriber [see Dosage and Administration (2.5)].

Driving or Operating Heavy Machinery

Inform patients that tramadol hydrochloride and acetaminophen tablets may impair the ability to perform potentially hazardous activities such as driving a car or operating heavy machinery. Advise patients not to perform such tasks until they know how they will react to the medication [see Warnings and Precautions (5.21)].

Constipation

Advise patients of the potential for severe constipation, including management instructions and when to seek medical attention [see Adverse Reactions (6)].

Adrenal Insufficiency

Inform patients that opioids could cause adrenal insufficiency, a potentially life-threatening condition. Adrenal insufficiency may present with non-specific symptoms and signs such as nausea, vomiting, anorexia, fatigue, weakness, dizziness, and low blood pressure. Advise patients to seek medical attention if they experience a constellation of these symptoms [see Warnings and Precautions (5.14)].

Hypotension

Inform patients that tramadol hydrochloride and acetaminophen tablets may cause orthostatic hypotension and syncope. Instruct patients how to recognize symptoms of low blood pressure and how to reduce the risk of serious consequences should hypotension occur (e.g., sit or lie down, carefully rise from a sitting or lying position) [see Warnings and Precautions (5.15)].

Anaphylaxis

Inform patients that anaphylaxis have been reported with ingredients contained in tramadol hydrochloride and acetaminophen tablets. Advise patients how to recognize such a reaction and when to seek medical attention [see Contraindications (4), Warnings and Precautions (5.19), Adverse Reactions (6)].

Pregnancy

Neonatal Opioid Withdrawal Syndrome

Inform female patients of reproductive potential that tramadol hydrochloride and acetaminophen tablets should not be used for more than 5 days and that use of opioids such as tramadol hydrochloride and acetaminophen tablets for an extended period of time, during pregnancy can result in neonatal opioid withdrawal syndrome, which may be life-threatening if not recognized and treated. The patient should inform their healthcare provider if they have used opioids at any time during their pregnancy [see Warnings and Precautions (5.4) and Use in Specific Populations (8.1)].

Embryo-Fetal Toxicity

Inform female patients of reproductive potential that tramadol hydrochloride and acetaminophen tablets can cause fetal harm and to inform the healthcare provider of a known or suspected pregnancy [see Use in Specific Populations (8.1)].

Lactation

Advise women that breastfeeding is not recommended during treatment with tramadol hydrochloride and acetaminophen tablets [see Use in Specific Populations (8.2)].

Infertility

Inform patients that use of opioids for an extended period of time may cause reduced fertility. It is not known whether these effects on fertility are reversible [Use in Specific Populations (8.3)].

Maximum Daily Acetaminophen Use

Advise patients not to take more than 4,000 milligrams of acetaminophen per day and call their doctor if they have taken more than the recommended dose [see Warnings and Precautions (5.9, 5.20)].

Use with Other Acetaminophen-Containing Products

Advise patients not to take tramadol hydrochloride and acetaminophen tablets in combination with other tramadol or acetaminophen-containing products, including over-the-counter preparations [see Warnings and Precautions (5.9, 5.20)].

Manufactured by:

Micro Labs Limited

Goa-403 722, INDIA.

Manufactured for:

Micro Labs USA, Inc.

Somerset, NJ 08873

Rev. 11/2025-01

Medication Guide

Tramadol Hydrochloride (TRAM-a-dol HYE-droe-KLOR-ide) and Acetaminophen (ass-eet-ah-MEE-noe-fen) Tablets, C-IV

Tramadol hydrochloride and acetaminophen tabletis:

- A strong prescription pain medicine that contains an opioid (narcotic) that is used for the short-term (five days or less) management of acute pain, when other pain treatments such as non-opioid pain medicines do not treat your pain well enough or you cannot tolerate them.
- An opioid pain medicine that can put you at risk for overdose and death. Even if you take your dose correctly as prescribed you are at risk for opioid addiction, abuse, and misuse that can lead to death.

Important information about tramadol hydrochloride and acetaminophentablet:

- Get emergency help or call 911 right away if you take too much tramadol hydrochloride and acetaminophen tablet (overdose).When you first start taking tramadol hydrochloride and acetaminophen tablet, when your dose is changed, or if you take too much (overdose), serious or life-threatening breathing problems that can lead to death may occur. Ask your healthcare provider about medicines like naloxone or nalmefene that can be used in an emergency to reverse an opioid overdose.
- Taking tramadol hydrochloride and acetaminophen tablet with other opioid medicines, benzodiazepines, gabapentinoids (gabapentin or pregabalin), alcohol, or other central nervous system depressants (including street drugs) can cause severe drowsiness, decreased awareness, breathing problems, coma, and death.
- Never give anyone else your tramadol hydrochloride and acetaminophen tablet. They could die from taking it. Selling or giving away tramadol hydrochloride and acetaminophen tablet is against the law.
- Store tramadol hydrochloride and acetaminophen tablet securely, out of sight and reach of children, and in a location not accessible by others, including visitors to the home.
- Get emergency help right away if you take more than 4,000 mg of acetaminophen in 1 day. Taking tramadol hydrochloride and acetaminophen tablet with other products that contain acetaminophen can lead to serious liver problems and death.

Important Information Guiding Use in Pediatric Patients:

- Do not give tramadol hydrochloride and acetaminophen tablets to a child younger than 12 years of age.
- Do not give tramadol hydrochloride and acetaminophen tablets to a child younger than 18 years of age after surgery to remove the tonsils and/or adenoids.
- Avoid giving tramadol hydrochloride and acetaminophen tablets to children between 12 to 18 years of age who have risk factors for breathing problems such as obstructive sleep apnea, obesity, or underlying lung problems.

Do not taketramadol hydrochloride and acetaminophen tabletif you have:

- Severe asthma, trouble breathing, or other lung problems.
- A bowel blockage or have narrowing of the stomach or intestines.
- An allergy to any of its ingredients (e.g., tramadol hydrochloride or acetaminophen).
- Taken a Monoamine Oxidase Inhibitor, MAOI, (medicine used for depression) within the last 14 days.

Before takingtramadol hydrochloride and acetaminophen tablet, tell your healthcare provider if you have a history of:

- head injury, seizures

- liver, kidney, thyroid problems

- problems urinating

- pancreas or gallbladder problems

- abuse of street or prescription drugs,

alcohol addiction, opioid overdose, or
mental health problems.

Tell your healthcare provider if you:

- noticing your pain getting worse. If your pain gets worse after you take tramadol hydrochloride and acetaminophen tablets, do not take more of tramadol hydrochloride and acetaminophen tablets without first talking to your healthcare provider. Talk to your healthcare provider if the pain that you have increases, if you feel more sensitive to pain, or if you have new pain after taking tramadol hydrochloride and acetaminophen tablets.
- Are pregnant or planning to become pregnant. Use of tramadol hydrochloride and acetaminophen tablet for an extended period of time during pregnancy can cause withdrawal symptoms in your newborn baby that could be life-threatening if not recognized and treated.
- breastfeeding. Not recommended; it may harm your baby.
- living in a household where there are small children or someone who has abused street or prescription drugs.
- taking prescription or over-the-counter medicines, vitamins, or herbal supplements. Taking tramadol hydrochloride and acetaminophen tablet with certain other medicines can cause serious side effects that could lead to death.

When takingtramadol hydrochloride and acetaminophen tablet:

- Do not change your dose. Take tramadol hydrochloride and acetaminophen tablet exactly as prescribed by your healthcare provider. Use the lowest dose possible for the shortest time needed.
- For acute (short-term) pain, you may only need to take tramadol hydrochloride and acetaminophen tablets for a few days. You may have some tramadol hydrochloride and acetaminophen tablets left over that you did not use. See disposal information at the bottom of this section for directions on how to safely throw away (dispose of) your unused tramadol hydrochloride and acetaminophen tablets.
- Take your prescribed dose: 2 tablets every 4 to 6 hours as needed for pain relief for a maximum of 5 days. Do not take more than your prescribed dose and do not take more than 8 tablets per day. If you miss a dose, take your next dose at your usual time.
- Call your healthcare provider if the dose you are taking does not control your pain.
- If you have been taking tramadol hydrochloride and acetaminophen tablet regularly, do not stop taking tramadol hydrochloride and acetaminophen tablet without talking to your healthcare provider.
- Dispose of expired, unwanted, or unused tramadol hydrochloride and acetaminophen tablets by taking your drug to an authorized Drug Enforcement Administration (DEA)-registered collector or drug take-back program. If one is not available, you can dispose of tramadol hydrochloride and acetaminophen tablets by mixing the product with dirt, cat litter, or coffee grounds; placing the mixture in a sealed plastic bag and throwing the bag in your trash. Visit www.fda.gov/drugdisposal for additional information on disposal of unused medicines.

While takingtramadol hydrochloride and acetaminophen tablet DO NOT:

- Drive or operate heavy machinery, until you know how tramadol hydrochloride and acetaminophen tablet affects you. Tramadol hydrochloride and acetaminophen tablet can make you sleepy, dizzy, or lightheaded.
- Drink alcohol or use prescription or over-the-counter medicines that contain alcohol. Using products containing alcohol during treatment with tramadol hydrochloride and acetaminophen tablet may cause you to overdose and die.

The possible side effects oftramadol hydrochloride and acetaminophen tablet:

- constipation, nausea, sleepiness, vomiting, tiredness, headache, dizziness, abdominal pain. Call your healthcare provider if you have any of these symptoms and they are severe.

Get emergency medical help or call 911 right away if you have:

- trouble breathing, shortness of breath, fast heartbeat, chest pain, swelling of your face, tongue, or throat, extreme drowsiness, light-headedness when changing positions, feeling faint, agitation, high body temperature, trouble walking, stiff muscles, or mental changes such as confusion.

These are not all the possible side effects of tramadol hydrochloride and acetaminophen tablet. Call your healthcare provider for medical advice about side effects. You may report side effects to FDA at 1-800-FDA-1088. For more information, go to dailymed.nlm.nih.gov

This Medication Guide has been approved by the U.S. Food and Drug Administration.

Manufactured by:

Micro Labs Limited

Goa-403 722, INDIA.

Manufactured for:

Micro Labs USA, Inc.

Somerset, NJ 08873

Rev. 10/2025

PACKAGE LABEL.PRINCIPAL DISPLAY PANEL

NDC 42571-119-01

Rx Only
Tramadol
Hydrochloride and
Acetaminophen
Tablets, USP C-IV
37.5 mg/325 mg
Dispense the enclosed Medication Guide
to each patient.
100 Tablets
MICRO LABS LIMITED

NDC 42571-119-23
Tramadol Hydrochloride and
Acetaminophen Tablets, USP CIV
37.5 mg/325 mg
Dispense the enclosed Medication Guide
to each patient.
Rx Only
80 (8 x10) Unit-Dose Tablets
MICRO LABS LIMITED